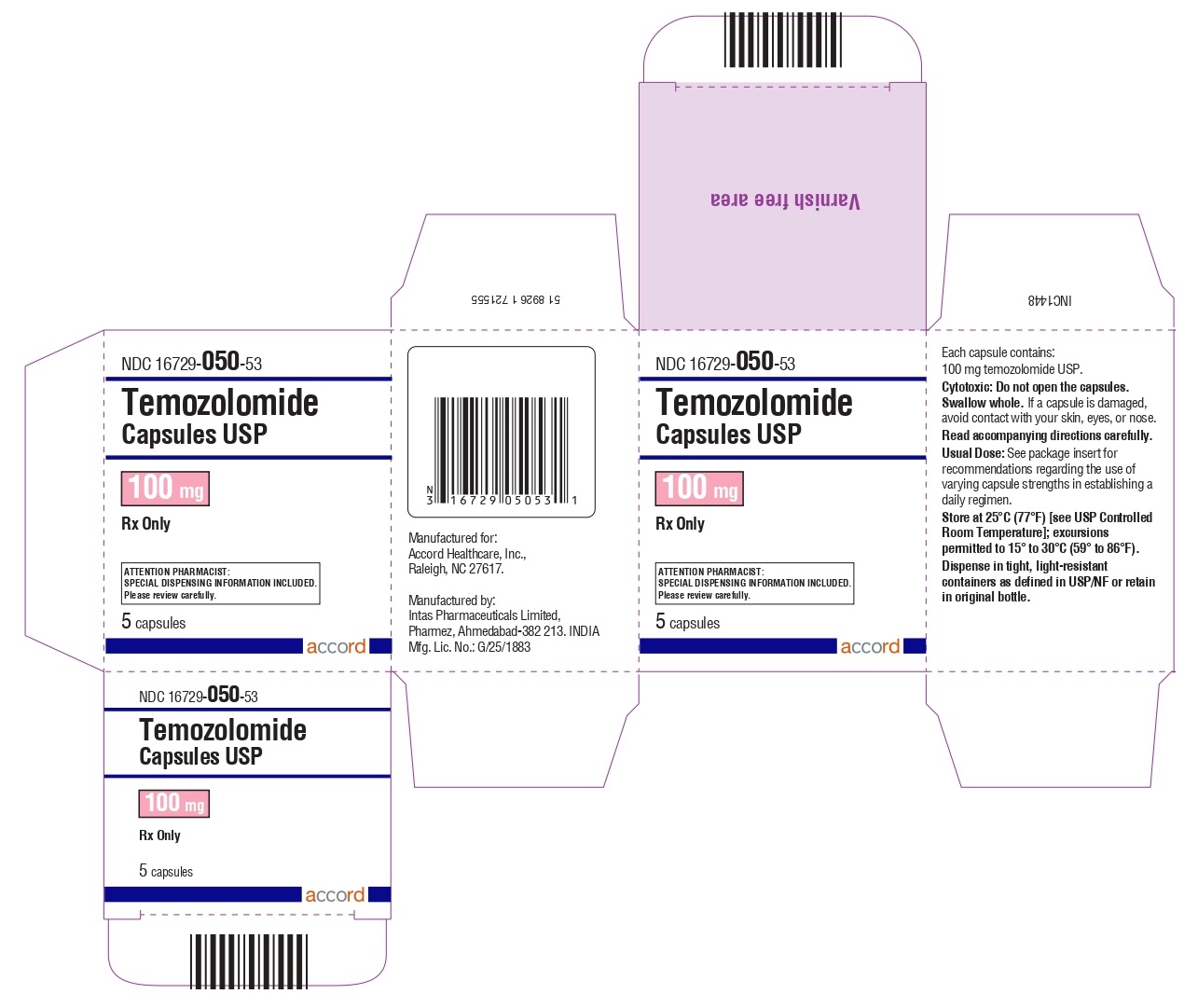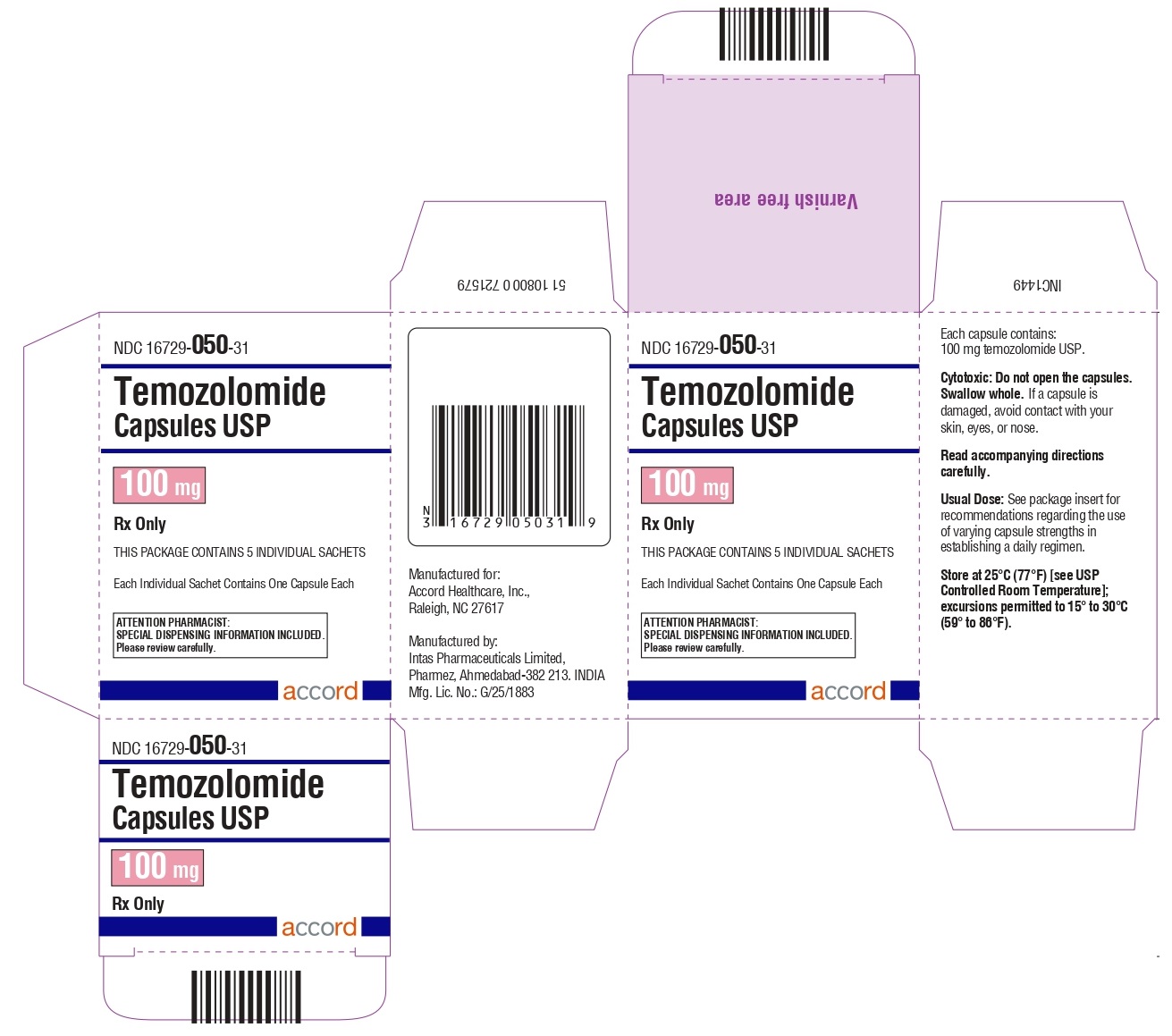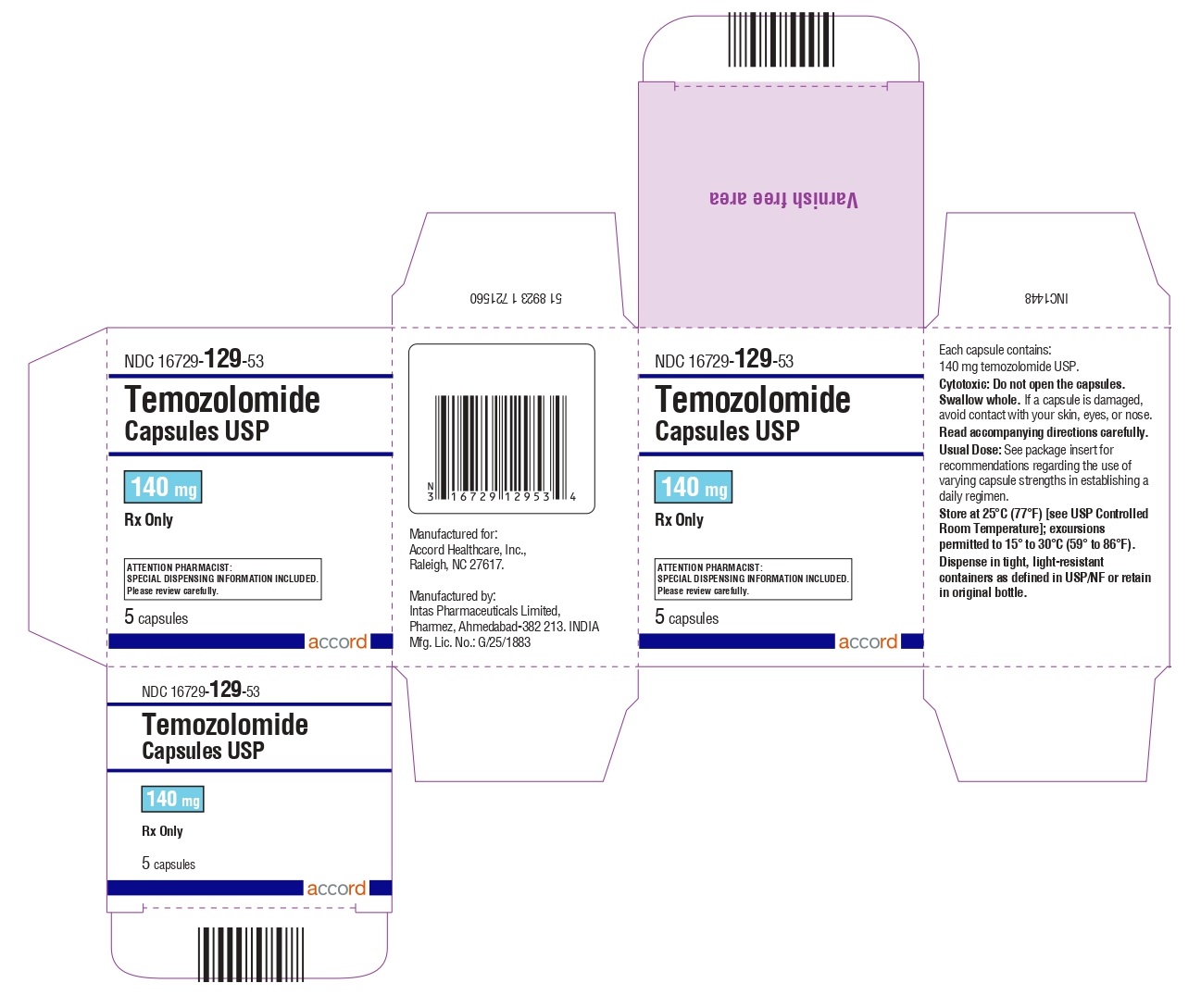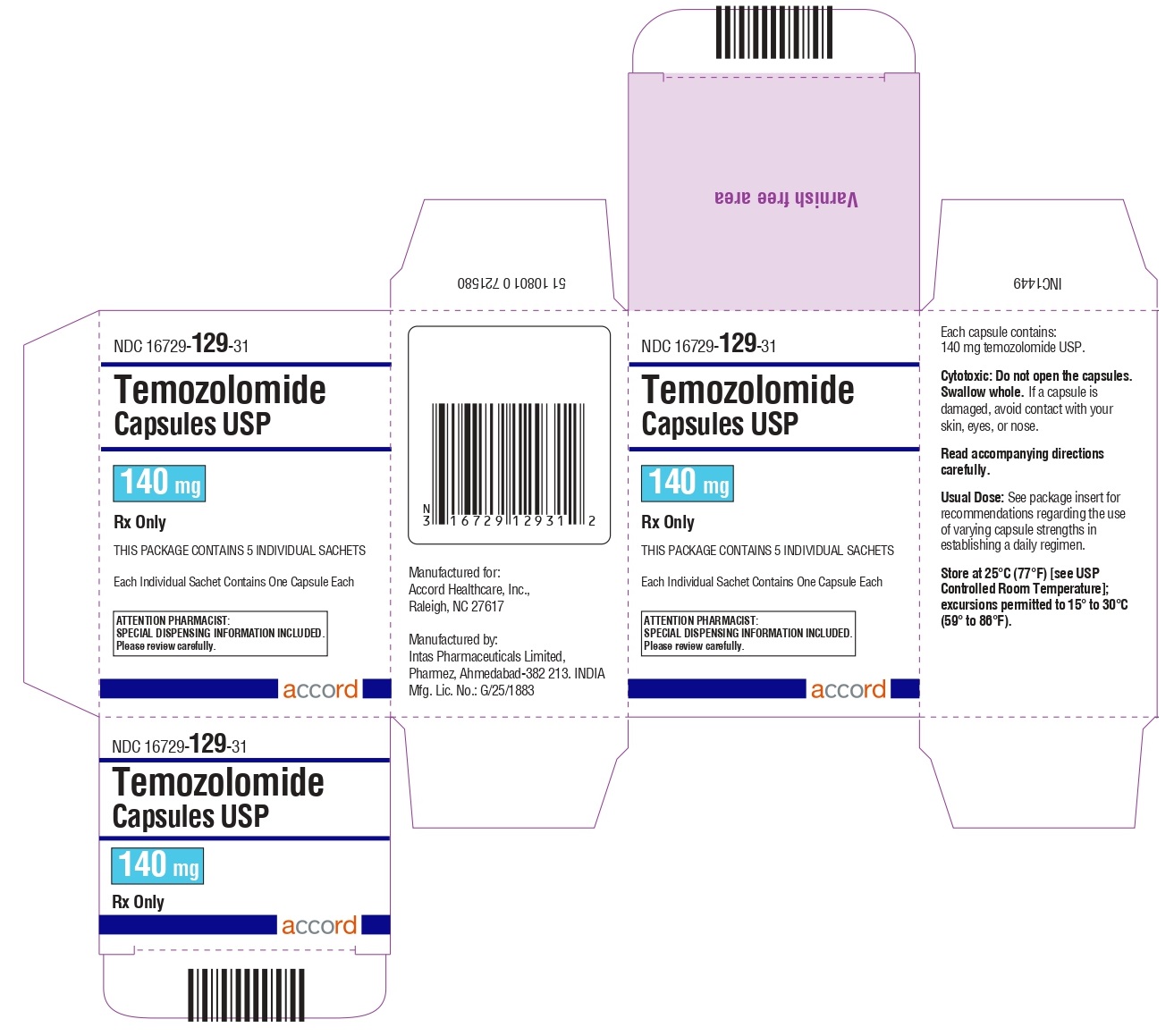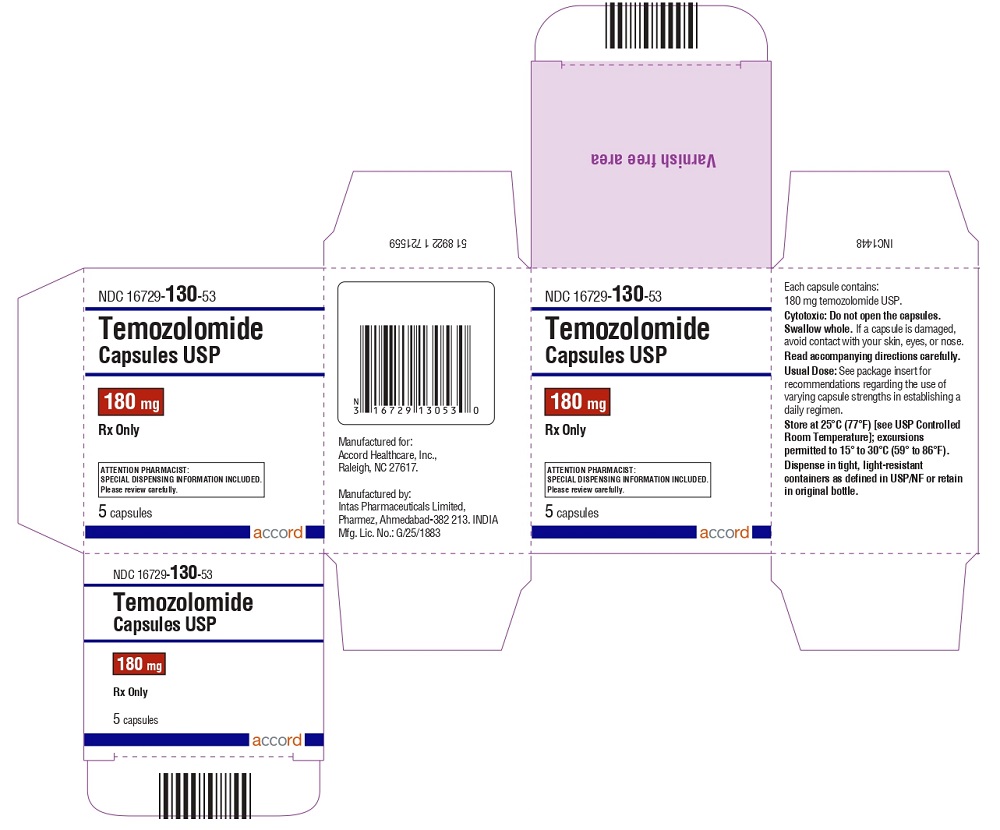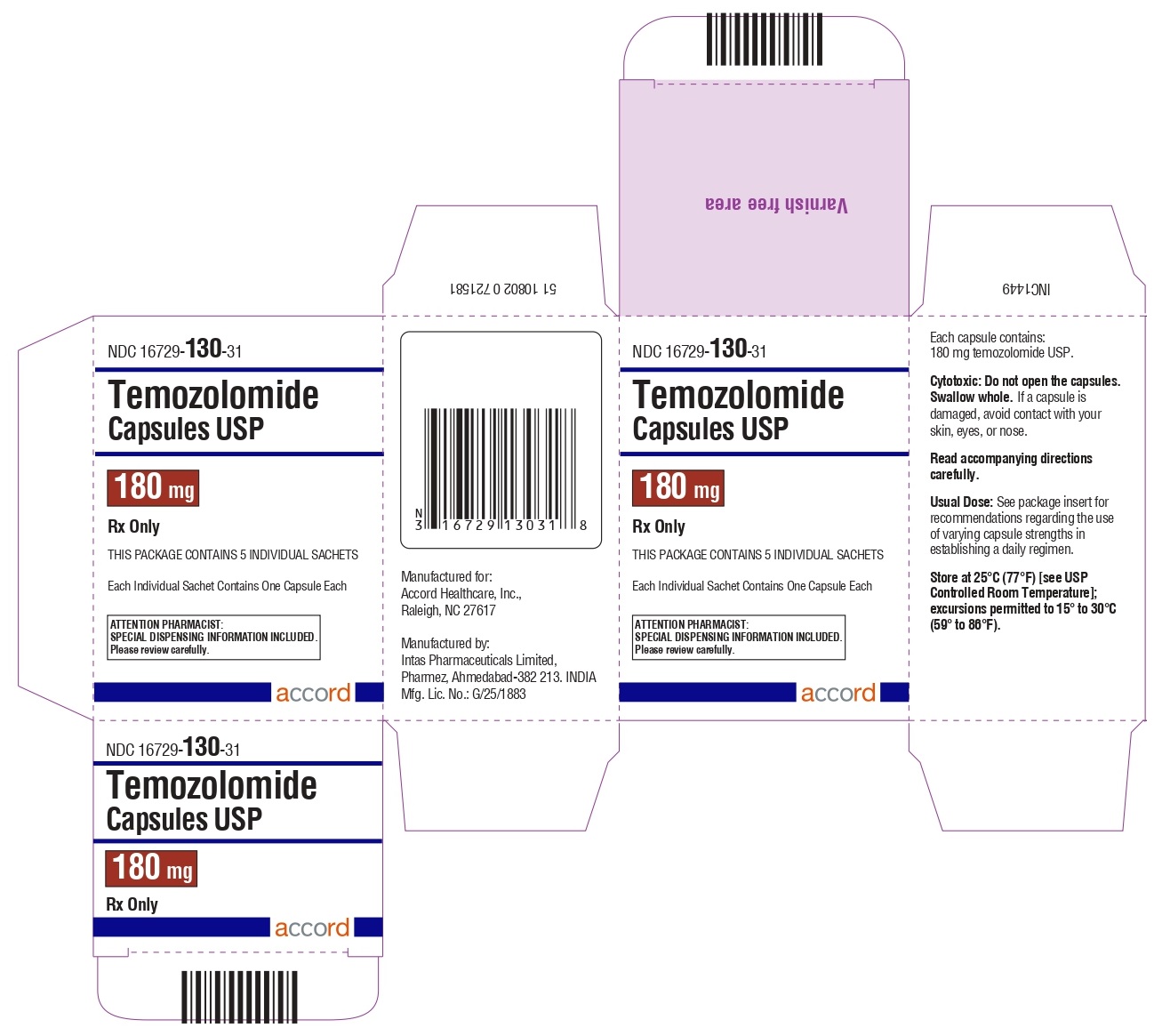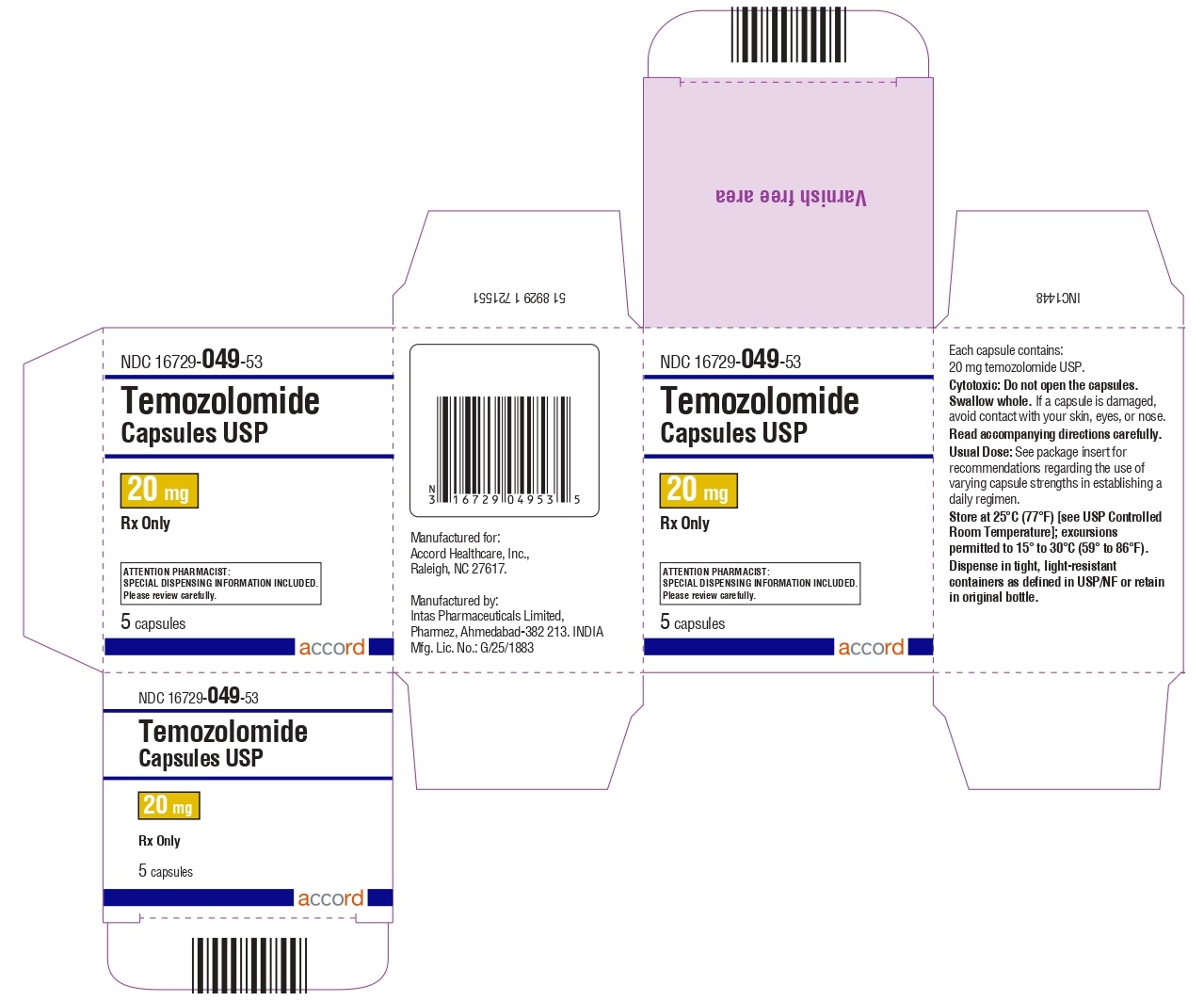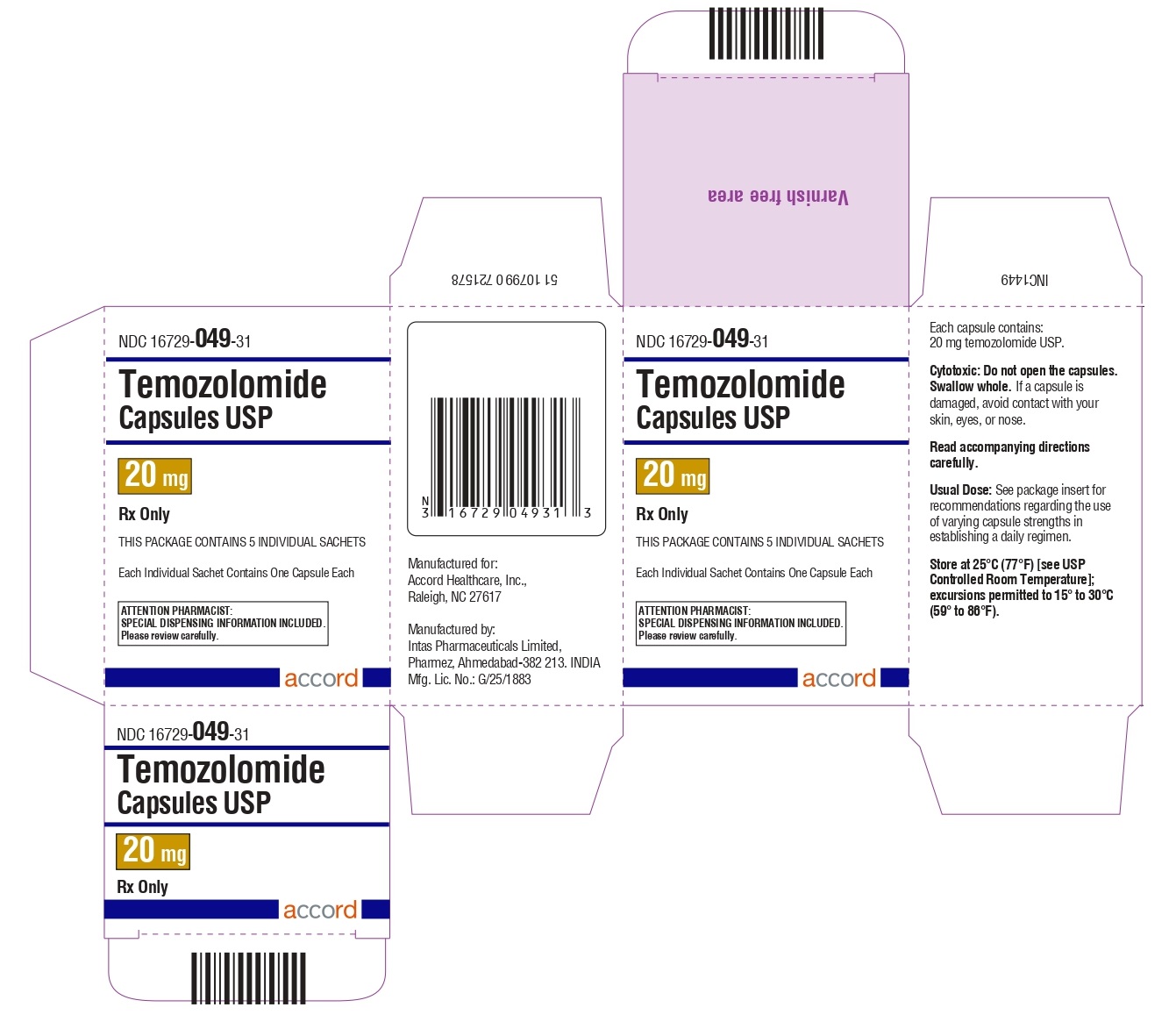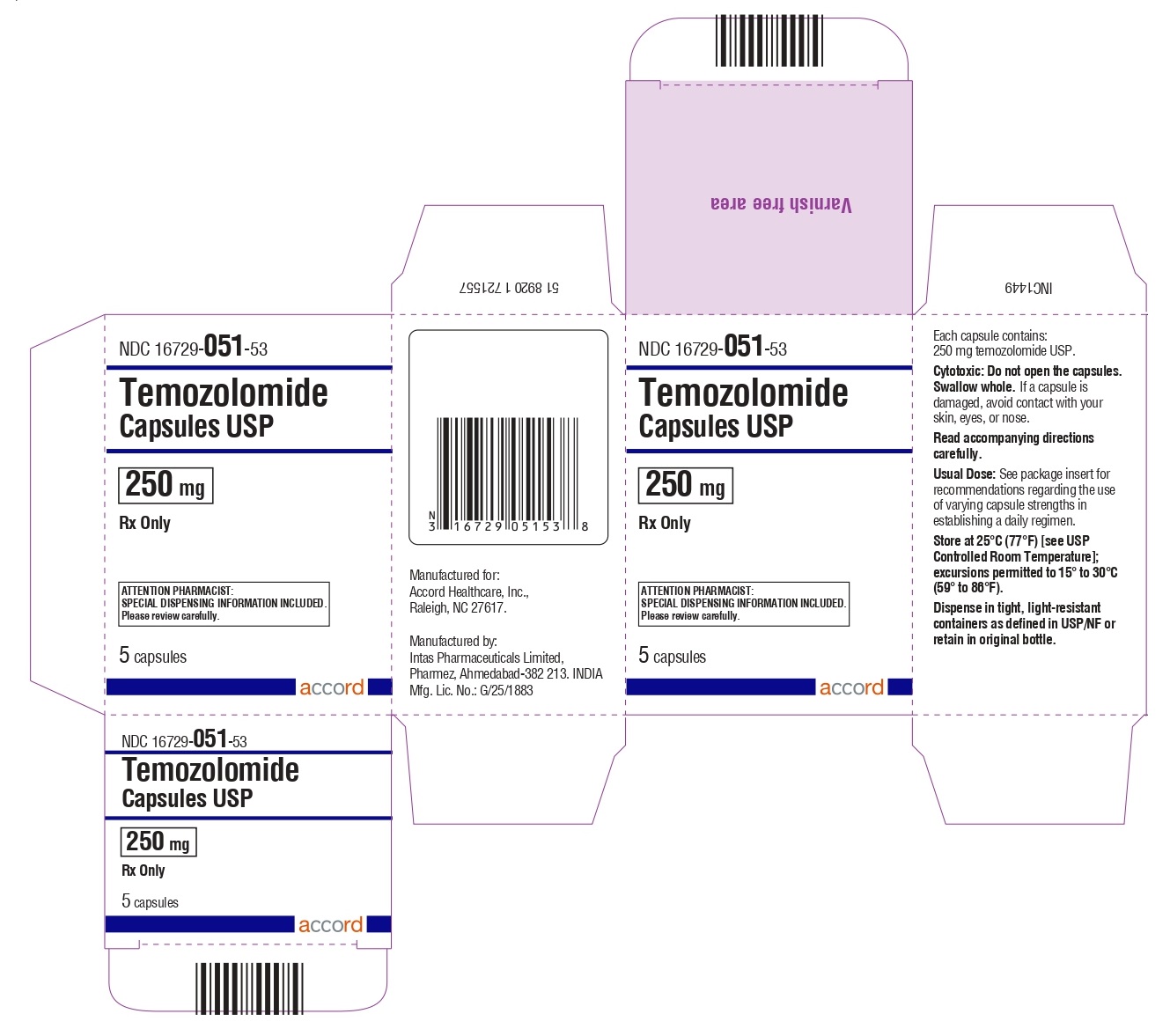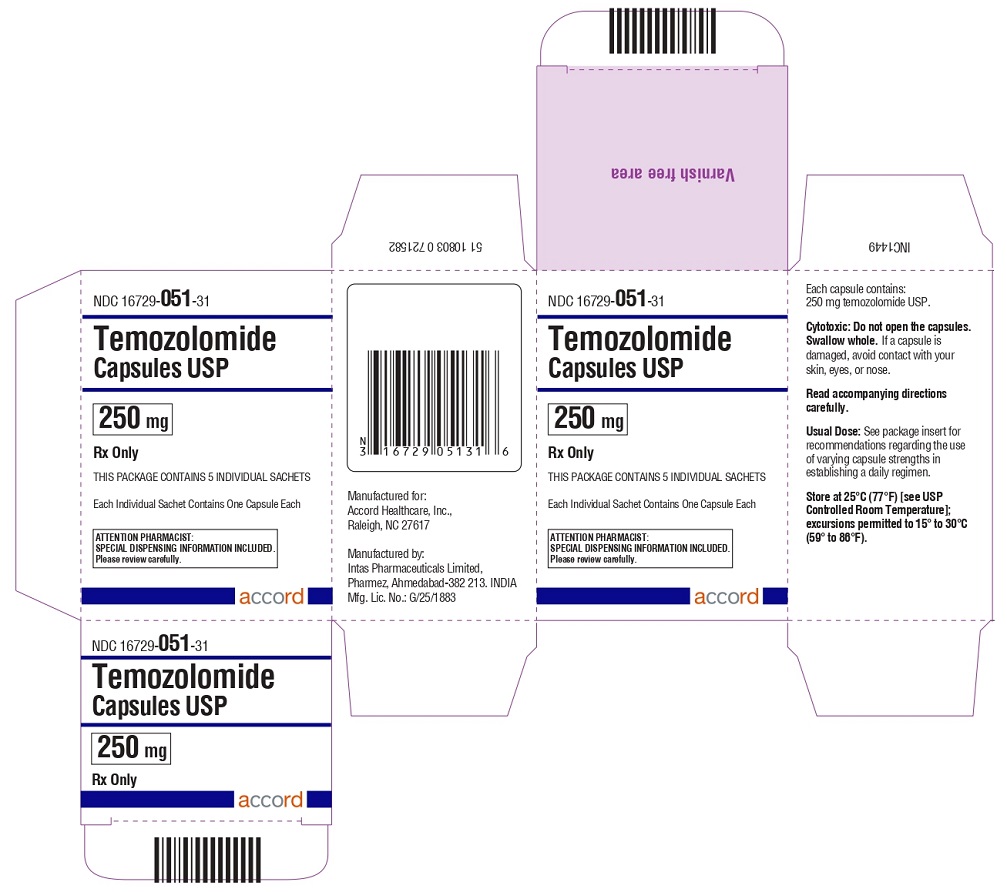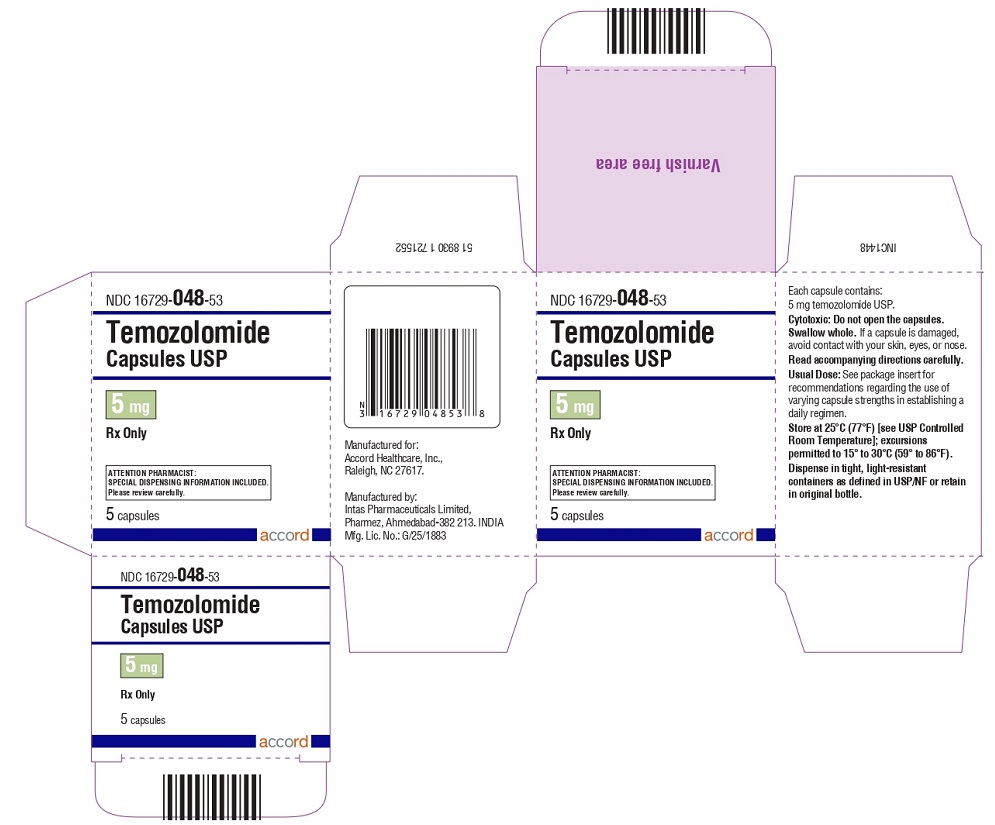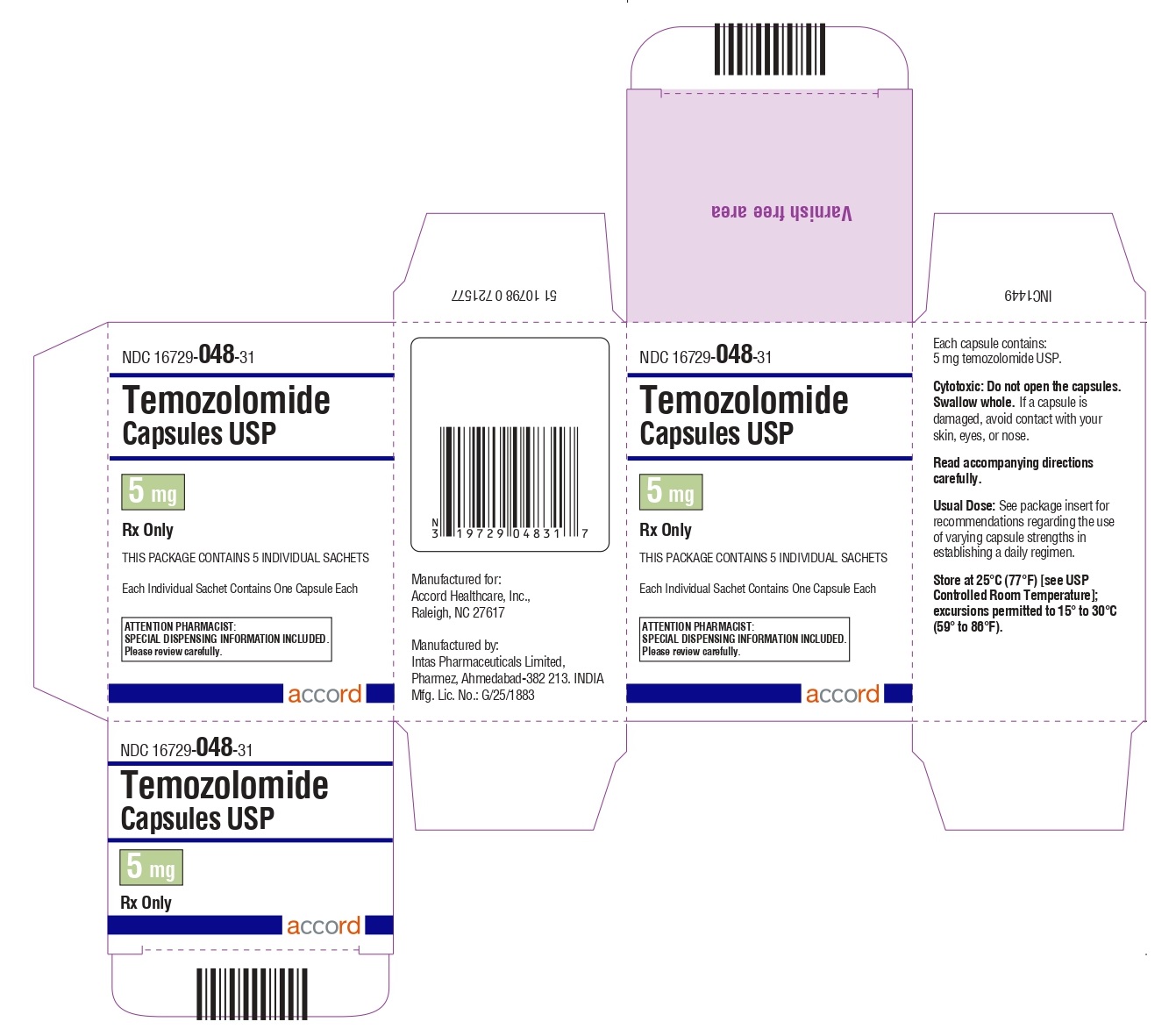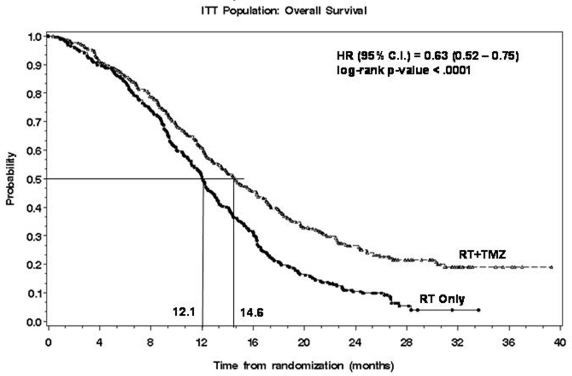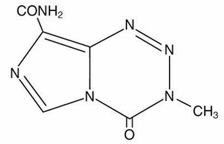 DRUG LABEL: Temozolomide
NDC: 16729-048 | Form: CAPSULE
Manufacturer: Accord Healthcare Inc.
Category: prescription | Type: HUMAN PRESCRIPTION DRUG LABEL
Date: 20250523

ACTIVE INGREDIENTS: TEMOZOLOMIDE 5 mg/1 1
INACTIVE INGREDIENTS: ANHYDROUS LACTOSE; SILICON DIOXIDE; SODIUM STARCH GLYCOLATE TYPE A POTATO; TARTARIC ACID; STEARIC ACID; FERRIC OXIDE RED; GELATIN; TITANIUM DIOXIDE; FERRIC OXIDE YELLOW; FD&C BLUE NO. 2; SHELLAC; POTASSIUM HYDROXIDE; FERROSOFERRIC OXIDE

HIGHLIGHTS OF PRESCRIBING INFORMATION

These highlights do not include all the information needed to use TEMOZOLOMIDE CAPSULES safely and effectively. See full prescribing information for TEMOZOLOMIDE CAPSULES.
TEMOZOLOMIDE capsules, for oral use
Initial U.S. Approval: 1999

RECENT MAJOR CHANGES

Indications and Usage (1.2) | 9/2023
Dosage and Administration (2.1, 2.2, 2.3, 2.4) | 9/2023
Contraindications (4) | 9/2023
Warnings and Precautions (5.1, 5.2, 5.4, 5.5, 5.6) | 9/2023

1 INDICATIONS AND USAGE

Temozolomide is an alkylating drug indicated for the treatment of adults with:

- Newly diagnosed glioblastoma concomitantly with radiotherapy and then as maintenance treatment. (1.1)
- Anaplastic astrocytoma. (1.2)
  - Adjuvant treatment of adults with newly diagnosed anaplastic astrocytoma.(1.2)
  - Treatment of adults with refractory anaplastic astrocytoma. (1.2)

2 DOSAGE AND ADMINISTRATION

- Administer either orally or intravenously.(2.4)
- Newly Diagnosed Glioblastoma:
  - 75 mg/m^2once daily for 42 to 49 days concomitant with focal radiotherapy followed by initial maintenance dose of 150 mg/m^2once daily for Days 1 to 5 of each 28-day cycle for 6 cycles. May increase maintenance dose to 200 mg/m^2for Cycles 2 to 6 based on toxicity. (2.1)
  - Provide Pneumocystis pneumonia (PCP) prophylaxis during concomitant phase and continue in patients who develop lymphopenia until resolution to Grade 1 or less. (2.1)
- Adjuvant Treatment of Newly Diagnosed Anaplastic Astrocytoma:
  Beginning 4 weeks after the end of radiotherapy, administer temozolomide capsules orally in a single dose on days 1-5 of a 28-day cycle for 12 cycles. The recommended dosage for Cycle 1 is 150 mg/m^2per day and for Cycles 2 to 12 is 200 mg/m^2if patient experienced no or minimal toxicity in Cycle 1. (2.2)
- Refractory Anaplastic Astrocytoma: Initial dose of 150 mg/m^2once daily on Days 1 to 5 of each 28-day cycle. (2.2)

3 DOSAGE FORMS AND STRENGTHS

- Capsules: 5 mg, 20 mg, 100 mg, 140 mg, 180 mg, and 250 mg. (3)

4 CONTRAINDICATIONS

- History of serious hypersensitivity to temozolomide or any other ingredients in temozolomide capsules and dacarbazine. (4)

5 WARNINGS AND PRECAUTIONS

- Myelosuppression: Monitor absolute neutrophil count (ANC) and platelet count prior to each cycle and during treatment. Geriatric patients and women have a higher risk of developing myelosuppression. (5.1, 8.5)
- Hepatotoxicity: Fatal and severe hepatotoxicity have been reported. Perform liver tests at baseline, midway through the first cycle, prior to each subsequent cycle, and approximately 2 to 4 weeks after the last dose of temozolomide. (5.2)
- Pneumocystis Pneumonia (PCP): Closely monitor all patients, particularly those receiving steroids, for the development of lymphopenia and PCP. (5.3)
- Secondary Malignancies:Myelodysplastic syndrome and secondary malignancies, including myeloid leukemia, have been observed. (5.4)
- Embryo-Fetal Toxicity: Can cause fetal harm. Advise females of reproductive potential of the potential risk to a fetus and to use effective contraception. Advise male patients with pregnant partners or female partners of reproductive potential to use condoms. (5.5, 8.1, 8.3)
- Exposure to Opened Capsules:Temozolomide capsules should not be opened, chewed, or dissolved but should be swallowed whole with a glass of water. (5.6)

6 ADVERSE REACTIONS

- The most common adverse reactions (≥20%) are: alopecia, fatigue, nausea, vomiting, headache, constipation, anorexia, and convulsions. (6.1)
- The most common Grade 3 to 4 hematologic laboratory abnormalities (≥10%) in patients with anaplastic astrocytoma are: decreased lymphocytes, decreased platelets, decreased neutrophils, and decreased leukocytes. (6.1)

To report SUSPECTED ADVERSE REACTIONS, contact Accord Healthcare Inc., at 1-866-941-7875 or FDA at 1-800-FDA-1088 or www.fda.gov/medwatch.

8 USE IN SPECIFIC POPULATIONS

- Lactation: Advise not to breastfeed. (8.2)

FULL PRESCRIBING INFORMATION

1 INDICATIONS AND USAGE

1.1 Newly Diagnosed Glioblastoma

Temozolomide capsule is indicated for the treatment of adults with newly diagnosed glioblastoma, concomitantly with radiotherapy and then as maintenance treatment.

1.2 Anaplastic Astrocytoma

Temozolomide capsule is indicated for the:

- adjuvant treatment of adults with newly diagnosed anaplastic astrocytoma;
- treatment of adults with refractory anaplastic astrocytoma

2 DOSAGE AND ADMINISTRATION

2.1 Monitoring to Inform Dosage and Administration

Prior to dosing, withhold temozolomide capsules until patients have an absolute neutrophil count (ANC) of 1.5 x 10^9/L or greater and a platelet count of 100 x 10^9/L or greater.

For concomitant radiotherapy, obtain a complete blood count prior to initiation of treatment and weekly during treatment. For the 28-day treatment cycles, obtain a complete blood count prior to treatment on Day 1 and on Day 22 of each cycle. Perform complete blood counts weekly until recovery if the ANC falls below 1.5 x 10^9/L and the platelet count falls below 100 x 10^9/L.

For concomitant use with focal radiotherapy, obtain a complete blood count weekly and as clinically indicated.

2.2 Recommended Dosage and Dosage Modifications for Newly Diagnosed Glioblastoma

Administer temozolomide capsules either orally or intravenously once daily for 42 to 49 consecutive days during the concomitant use phase with focal radiotherapy, and then once daily on Days 1 to 5 of each 28-day cycle for 6 cycles during the maintenance use phase.
Provide Pneumocystis pneumonia (PCP) prophylaxis during the concomitant use phase and continue in patients who develop lymphopenia until resolution to Grade 1 or less [see Warnings and Precautions (5.3)] .

Concomitant Use Phase:

The recommended dosage of temozolomide capsule is 75 mg/m^2orally once daily for 42 to 49 days in combination with focal radiotherapy. Focal radiotherapy includes the tumor bed or resection site with a 2 to 3 cm margin.

Other administration schedules have been used.

Obtain a complete blood count weekly. The recommended dosage modifications due to adverse reactions during concomitant use phase are provided in Table 1.

TABLE 1:Dosage Modifications Due to Adverse Reactions During Concomitant Use Phase
Adverse Reaction | Interruption | Discontinuation
Absolute Neutrophil Count | Withhold temozolomide if ANC is greater than or equal to 0.5 x 10^9/L and less than 1.5 x 10^9/L.; Resume temozolomide at the same dose when ANC is greater than or equal to 1.5 x 10^9/L. | Discontinue temozolomide if ANC count is less than 0.5 x 10^9/L.
Platelet Count | Withhold temozolomide if platelet count is greater than or equal to 10 x 10^9/L and less than 100 x 10^9/L.; Resume temozolomide at the same dose when platelet count is greater than or equal to 100 x 10^9/L. | Discontinue temozolomide if platelet count is less than 10 x 10^9/L.
Non-hematological Adverse Reaction (except for alopecia, nausea, vomiting) | Withhold temozolomide if Grade 2 adverse reaction occurs.; Resume temozolomide at the same dose when resolution to Grade 1 or less. | Discontinue temozolomide if Grade 3 or 4 adverse reaction occurs.

Single Agent Maintenance Use Phase:

Beginning 4 weeks after concomitant use phase completion, administer temozolomide capsules orally once daily on Days 1 to 5 of each 28-day cycle for 6 cycles. The recommended dosage of temozolomide capsules in the maintenance use phase is:

- Cycle 1: 150 mg/m^2per day on days 1 to 5.
- Cycles 2 to 6: May increase to 200 mg/m^2per day on days 1 to 5 before starting Cycle 2 if no dosage interruptions or discontinuations are required (Table 1). If the dose is not escalated at the onset of Cycle 2, do notincrease the dose for Cycles 3 to 6.

Obtain a complete blood count on Day 22 and then weekly until the ANC is above 1.5 x 10^9/L and the platelet count is above 100 x 10^9/L. Do not start the next cycle until the ANC and platelet count exceed these levels.

The recommended dosage modifications due to adverse reactions during the maintenance use phase are provided in Table 2.

If temozolomide is withheld, reduce the dose for the next cycle by 50 mg/m^2per day. Permanently discontinue temozolomide in patients who are unable to tolerate a dose of 100 mg/m^2per day.

TABLE 2: Dosage Modifications Due to Adverse Reactions During Maintenance and Adjuvant Treatment
Adverse Reactions | Interruption and Dose Reduction | Discontinuation
Absolute Neutrophil Count | Withhold temozolomide if ANC less than 1 x 10^9/L. When ANC is above 1.5 x 10^9/L, resume temozolomide at reduced dose for the next cycle. | Discontinue temozolomide if unable to tolerate a dose of 100 mg/m^2per day.
Platelet Count | Withhold temozolomide if platelet less than 50 x 10^9/L.; When platelet count is above 100 x 10^9/L, resume temozolomide at reduced dose for the next cycle. | Discontinue temozolomide if unable to tolerate a dose of 100 mg/m^2per day.
Nonhematological Adverse Reaction (except for alopecia, nausea, vomiting) | Withhold temozolomide if Grade 3 adverse reaction occurs. When resolved to Grade 1 or less, resume temozolomide at reduced dose for the next cycle. | Discontinue temozolomide if recurrent Grade 3 adverse reaction occurs after dose reduction, if Grade 4 adverse reaction occurs, or if unable to tolerate a dose of 100mg/m^2per day.

2.3 Recommended Dosage and Dosage Modifications for Anaplastic Astrocytoma

Adjuvant Treatment of Newly Diagnosed Anaplastic Astrocytoma

Beginning 4 weeks after the end of radiotherapy, administer temozolomide capsules orally in a single dose on days 1 to 5 of a 28-day cycle for 12 cycles. The recommended dosage of temozolomide capsule is:

- Cycle 1: 150 mg/m^2per day on days 1 to 5.
- Cycles 2 to 12: 200 mg/m^2per day on days 1 to 5 if patient experienced no or minimal toxicity in Cycle 1. If the dose was not escalated at the onset of Cycle 2, do not increase the dose during Cycles 3 to 6.

The recommended complete blood count testing and dosage modifications due to adverse reactions during adjuvant treatment are provided above and in Table 2 [see Dosage and Administration (2.2)].

Refractory Anaplastic Astrocytoma

The recommended initial dosage of temozolomide is 150 mg/m^2once daily on Days 1 to 5 of each 28-day cycle. Increase the temozolomide dose to 200 mg/m^2per day if the following conditions are met at the nadir and on Day 1 of the next cycle:

- ANC is greater than or equal to 1.5 x 10^9/L and
- Platelet count is greater than or equal to 100 x 10^9/L

Continue temozolomide until disease progression or unacceptable toxicity.

Obtain a complete blood count on Day 22 and then weekly until the ANC is above 1.5 x 10^9/L and the platelet count is above 100 x 10^9/L. Do not start the next cycle until the ANC and platelet count exceed these levels.

If the ANC is less than 1 x 10^9/L or the platelet count is less than 50 x 10^9/L during any cycle, reduce the temozolomide dose for the next cycle by 50 mg/m^2per day. Permanently discontinue temozolomide in patients who are unable to tolerate a dose of 100 mg/m^2per day.

2.4 Preparation and Administration

Temozolomide is a hazardous drug. Follow applicable special handling and disposal procedures.^1

Temozolomide capsules

Take temozolomide capsules at the same time each day. Administer temozolomide capsules consistently with respect to food (fasting vs. nonfasting) [see Clinical Pharmacology (12.3)]. To reduce nausea and vomiting, take temozolomide capsules on an empty stomach or at bedtime and consider antiemetic therapy prior to and following temozolomide capsules administration.

Swallow temozolomide capsules whole with water. Advise patients not to open, chew or dissolve the contents of the capsules [see Warning and Precautions (5.6)].

If capsules are accidentally opened or damaged, take precautions to avoid inhalation or contact with the skin or mucous membranes. In case of powder contact, wash the affected area with water immediately.

3 DOSAGE FORMS AND STRENGTHS

- Temozolomide capsules, USP for oral administration
  - 5-mg capsules have white bodies with green caps. The capsule body is imprinted with '5'. The cap is imprinted with 'TMZ'.
  - 20-mg capsules have white bodies with yellow caps. The capsule body is imprinted with '20'. The cap is imprinted with 'TMZ'.
  - 100-mg capsules have white bodies with pink caps. The capsule body is imprinted with '100'. The cap is imprinted with 'TMZ'.
  - 140-mg capsules have white bodies with transparent blue caps. The capsule body is imprinted with '140'. The cap is imprinted with 'TMZ'.
  - 180-mg capsules have white bodies with maroon caps. The capsule body is imprinted with '180'. The cap is imprinted with 'TMZ'.
  - 250-mg capsules have white bodies with white caps. The capsule body is imprinted with '250'. The cap is imprinted with 'TMZ'.

4 CONTRAINDICATIONS

Temozolomide is contraindicated in patients with a history of serious hypersensitivity reactions to:

- temozolomide or any other ingredients in temozolomide capsules; and
- dacarbazine, since both temozolomide and dacarbazine are metabolized to the same active metabolite 5-(3methyltriazen-1-yl)-imidazole-4-carboxamide.

Reactions to temozolomide have included anaphylaxis [see Adverse Reactions (6.2)].

5 WARNINGS AND PRECAUTIONS

5.1 Myelosuppression

Myelosuppression, including pancytopenia, leukopenia and anemia, some with fatal outcomes, have occurred with temozolomide [see Adverse Reactions (6.1, 6.2)].

In MK-7365-006, myelosuppression usually occurred during the first few cycles of therapy and was generally not cumulative. The median nadirs occurred at 26 days for platelets (range: 21 to 40 days) and 28 days for neutrophils (range: 1 to 44 days). Approximately 10% of patients required hospitalization, blood transfusion, or discontinuation of therapy due to myelosuppression. Geriatric patients and women have been shown in clinical trials to have a higher risk of developing myelosuppression.

Obtain a complete blood count and monitor ANC and platelet counts before initiation of treatment and as clinically indicated during treatment. When temozolomide is used in combination with radiotherapy, obtain a complete blood count prior to initiation of treatment, weekly during treatment, and as clinically indicated [see Dosage and Administration (2.1, 2.2, 2.3)].

For severe myelosuppression, withhold temozolomide and then resume at same or reduced dose, or permanently discontinue, based on occurrence [see Dosage and Administration (2.1, 2.2, 2.3)].

5.2 Hepatotoxicity

Fatal and severe hepatotoxicity have been reported in patients receiving temozolomide. Perform liver tests at baseline, midway through the first cycle, prior to each subsequent cycle, and approximately two to four weeks after the last dose of temozolomide.

5.3 Pneumocystis Pneumonia

Pneumocystis pneumonia (PCP) has been reported in patients receiving temozolomide. The risk of PCP is increased in patients receiving steroids or with longer treatment regimens of temozolomide.

For patients with newly diagnosed glioblastoma, provide PCP prophylaxis for all patients during the concomitant phase. Continue PCP prophylaxis in patients who experience lymphopenia, until resolution to Grade 1 or less [see Dosage and Administration (2.1)].

Monitor all patients receiving temozolomide for the development of lymphopenia and PCP.

5.4 Secondary Malignancies

The incidence of secondary malignancies is increased in patients treated with temozolomide-containing regimens. Cases of myelodysplastic syndrome and secondary malignancies, including myeloid leukemia, have been observed following temozolomide administration.

5.5 Embryo-Fetal Toxicity

Based on findings from animal studies and its mechanism of action, temozolomide can cause fetal harm when administered to a pregnant woman. Adverse developmental outcomes have been reported in both pregnant patients and pregnant partners of male patients. Oral administration of temozolomide to rats and rabbits during the period of organogenesis resulted in embryolethality and polymalformations at doses less than the maximum human dose based on body surface area.

Advise pregnant women and females of reproductive potential of the potential risk to a fetus. Advise females of reproductive potential to use effective contraception during treatment with temozolomide and for 6 months after the last dose. Because of potential risk of genotoxic effects on sperm, advise male patients with female partners of reproductive potential to use condoms during treatment with temozolomide and for 3 months after the last dose. Advise male patients not to donate semen during treatment with temozolomide and for 3 months after the last dose [see Use in Specific Populations (8.1, 8.3)].

5.6 Exposure to Opened Capsules

Advise patients not to open, chew or dissolve the contents of the temozolomide capsules. Swallow capsules whole with a glass of water. If a capsule becomes damaged, avoid contact of the powder contents with skin or mucous membranes. In case of powder contact, wash affected area with water immediately [see Dosage and Administration (2.4)]. If temozolomide capsules must be opened or the contents must be dissolved, this should be done by a professional trained in safe handling of hazardous drugs using appropriate equipment and safety procedures.

6 ADVERSE REACTIONS

The following clinically significant adverse reactions are described elsewhere in the labeling:

- Myelosuppression [see Warnings and Precautions (5.1)] .
- Hepatotoxicity [see Warnings and Precautions (5.2)] .
- Pneumocystis Pneumonia [see Warnings and Precautions (5.3)] .
- Secondary Malignancies [see Warnings and Precautions (5.4)] .

6.1 Clinical Trials Experience

Because clinical trials are conducted under widely varying conditions, adverse reaction rates observed in the clinical trials of a drug cannot be directly compared to rates in the clinical trials of another drug and may not reflect the rates observed in practice.

Newly Diagnosed Glioblastoma

The safety of temozolomide was evaluated in study MK-7365-051 [see Clinical Studies (14.1)] .

Severe or life-threatening adverse reactions occurred in 49% of patients treated with temozolomide; the most common were fatigue (13%), convulsions (6%), headache (5%), and thrombocytopenia (5%).

The most common adverse reactions (≥20%) in patients treated with temozolomide were alopecia, fatigue, nausea, anorexia, headache, constipation, and vomiting.

Table 3 summarizes the adverse reactions in MK-7365-051.

TABLE 3: Adverse Reactions (≥10%) in Patients with Newly Diagnosed Glioblastoma
Adverse Reactions | Concomitant Use Phase |  |  |  | Maintenance Use Phase
Adverse Reactions | Radiation Therapy and Temozolomide; N=288* |  | Radiation Therapy Alone; N=285 |  | Temozolomide; N=224
Adverse Reactions | All Grades; (%) | Grade ≥3 (%) | All Grades; (%) | Grade ≥3 (%) | All Grades; (%) | Grade ≥3 (%)
Skin and Subcutaneous Tissue
Alopecia | 69 | 0 | 63 | 0 | 55 | 0
Rash | 19 | 1 | 15 | 0 | 13 | 1
General
Fatigue | 54 | 7 | 49 | 5 | 61 | 9
Anorexia | 19 | 1 | 9 | <1 | 27 | 1
Headache | 19 | 2 | 17 | 4 | 23 | 4
Gastrointestinal System
Nausea | 36 | 1 | 16 | <1 | 49 | 1
Vomiting | 20 | <1 | 6 | <1 | 29 | 2
Constipation | 18 | 1 | 6 | 0 | 22 | 0
Diarrhea | 6 | 0 | 3 | 0 | 10 | 1
Central and Peripheral Nervous System
Convulsions | 6 | 3 | 7 | 3 | 11 | 3

*One patient who was randomized to radiation therapy-only arm received radiation therapy and temozolomide.

NOS=not otherwise specified.

Note:Grade 5 (fatal) adverse reactions are included in the Grade ≥3 column.

Clinically relevant adverse reactions in <10% of patients are presented below:

Central & Peripheral Nervous System:memory impairment, confusion

Eye:vision blurred

Gastrointestinal System:stomatitis, abdominal pain

General:weakness, dizziness Immune System: allergic reaction

Injury:radiation injury not otherwise specified

Musculoskeletal System:arthralgia

Platelet, Bleeding, & Clotting:thrombocytopenia

Psychiatric:insomnia

Respiratory System:coughing, dyspnea

Special Senses Other:taste perversion

Skin & Subcutaneous Tissue:dry skin, pruritus, erythema

When laboratory abnormalities and adverse reactions were combined, Grade 3 or Grade 4 neutrophil abnormalities including neutropenic reactions were observed in 8% of patients, and Grade 3 or Grade 4 platelet abnormalities including thrombocytopenic reactions were observed in 14% of patients.

Newly Diagnosed Anaplastic Astrocytoma

The safety of temozolomide for the adjuvant treatment of adults with newly diagnosed anaplastic astrocytoma was derived from published literature [see Clinical Studies (14.2)] .The safety of temozolomide for the adjuvant treatment of patients with newly diagnosed anaplastic astrocytoma was consistent with the known safety profile of temozolomide.

Refractory Anaplastic Astrocytoma

The safety of temozolomide was evaluated in study MK-7365-006 [see Clinical Studies (14.2)] .

The most common adverse reactions (≥20%) were nausea, vomiting, headache, fatigue, constipation, and convulsions.

Tables 4and 5summarize the adverse reactions and hematological laboratory abnormalities in MK-7365-006.

TABLE 4: Adverse Reactions (≥10%) in Patients with Refractory Anaplastic Astrocytoma
Adverse Reactions | Temozolomide; N=158
Adverse Reactions | All Reactions; (%) | Grade 3 to 4; (%)
Gastrointestinal System
Nausea | 53 | 10
Vomiting | 42 | 6
Constipation | 33 | 1
Diarrhea | 16 | 2
General
Headache | 41 | 6
Fatigue | 34 | 4
Asthenia | 13 | 6
Fever | 13 | 2
Central and Peripheral Nervous System
Convulsions | 23 | 5
Hemiparesis | 18 | 6
Dizziness | 12 | 1
Coordination abnormal | 11 | 1
Amnesia | 10 | 4
Insomnia | 10 | 0
Cardiovascular
Edema peripheral | 11 | 1
Resistance Mechanism
Infection viral | 11 | 0

Clinically relevant adverse reactions in <10% of patients are presented below:

Central and Peripheral Nervous System:paresthesia, somnolence, paresis, urinary incontinence, ataxia, dysphasia, convulsions local, gait abnormal, confusion

Endocrine:adrenal hypercorticism

Gastrointestinal System:abdominal pain, anorexia

General: back pain

Metabolic:weight increase

Musculoskeletal System:myalgia

Psychiatric:anxiety, depression

Reproductive Disorders:breast pain female

Respiratory System:upper respiratory tract infection, pharyngitis, sinusitis, coughing

Skin & Appendages:rash, pruritus

Urinary System:urinary tract infection, micturition increased frequency

Vision:diplopia, vision abnormal*

*This term includes blurred vision; visual deficit; vision changes; and vision troubles.

TABLE 5: Grade 3 to 4 Hematologic Laboratory Abnormalities That Worsened from Baseline in Patients with Refractory Anaplastic Astrocytoma
 | Temozolomide*,† (%)
Decreased lymphocytes | 55
Decreased platelets | 19
Decreased neutrophils | 14
Decreased leukocytes | 11
Decreased hemoglobin | 4

* Change from Grade 0 to 2 at baseline to Grade 3 or 4 during treatment.

† Denominator range = 142, 158

Hematological Toxicities for Advanced Gliomas

In clinical trial experience with 110 to 111 females and 169 to 174 males (depending on measurements), females experienced higher rates of Grade 4 neutropenia (ANC < 0.5 x 10^9/L) and thrombocytopenia (< 20 x 10^9/L) than males in the first cycle of therapy (12% vs. 5% and 9% vs. 3%, respectively).

In the entire safety database for which hematologic data exist (N=932), 7% (4/61) and 10% (6/63) of patients > 70 years experienced Grade 4 neutropenia or thrombocytopenia in the first cycle, respectively. For patients ≤ 70 years, 7% (62/871) and 6% (48/879) experienced Grade 4 neutropenia or thrombocytopenia in the first cycle, respectively. Pancytopenia, leukopenia, and anemia also occurred.

6.2 Postmarketing Experience

The following adverse reactions have been identified during post-approval use of temozolomide. Because these reactions are reported voluntarily from a population of uncertain size, it is not always possible to reliably estimate their frequency or establish a causal relationship to the drug exposure.

Dermatologic:Toxic epidermal necrolysis and Stevens-Johnson syndrome.

Immune System:Hypersensitivity reactions, including anaphylaxis. Erythema multiforme, which resolved after discontinuation of temozolomide capsules and, in some cases, recurred upon rechallenge.

Hematopoietic:Prolonged pancytopenia, which may result in aplastic anemia and fatal outcomes.

Hepatobiliary:Fatal and severe hepatotoxicity, elevation of liver enzymes, hyperbilirubinemia, cholestasis, and hepatitis.

Infections:Serious opportunistic infections, including some cases with fatal outcomes with bacterial, viral (primary and reactivated), fungal, and protozoan organisms.

Pulmonary:Interstitial pneumonitis, pneumonitis, alveolitis, and pulmonary fibrosis.

Endocrine:Diabetes insipidus.

8 USE IN SPECIFIC POPULATIONS

8.1 Pregnancy

Risk Summary

Based on findings from animal studies and its mechanism of action [see Clinical Pharmacology (12.1)] and findings from animal studies, temozolomide can cause fetal harm when administered to a pregnant woman. Available postmarketing reports describe cases of spontaneous abortions and congenital malformations, including polymalformations with central nervous system, facial, cardiac, skeletal, and genitourinary system anomalies with exposure to temozolomide during pregnancy. These cases report similar adverse developmental outcomes to those observed in animal studies. Administration of temozolomide to rats and rabbits during the period of organogenesis caused numerous external, internal, and skeletal malformations at doses less than the maximum human dose based on body surface area (see Data). Advise pregnant women of the potential risk to a fetus.

In the U.S. general population, the estimated background risk of major birth defects and miscarriage in clinically recognized pregnancies is 2% to 4% and 15% to 20%, respectively.

Data

Animal Data

Five consecutive days of oral administration of temozolomide at doses of 75 and 150 mg/m^2(0.38 and 0.75 times the human dose of 200 mg/m^2) in rats and rabbits, respectively, during the period of organogenesis (Gestation Days 8 to 12) caused numerous malformations of the external and internal organs and skeleton in both species. In rabbits, temozolomide at the 150 mg/m^2dose (0.75 times the human dose of 200 mg/m^2) caused embryolethality as indicated by increased resorptions.

8.2 Lactation

There are no data on the presence of temozolomide or its metabolites in human milk, the effects on a breastfed child, or the effects on milk production. Because of the potential for serious adverse reactions, including myelosuppression from temozolomide in the breastfed children, advise women not to breastfeed during treatment with temozolomide and for 1 week after the last dose.

8.3 Females and Males of Reproductive Potential

Temozolomide can cause fetal harm when administered to a pregnant woman [see Use in Specific Populations (8.1)].

Pregnancy Testing

Verify pregnancy status in females of reproductive potential prior to initiating temozolomide [see Use in Specific Populations (8.1)].

Contraception

Females

Advise females of reproductive potential to use effective contraception during treatment with temozolomide and for 6 months after the last dose.

Males

Because of the potential for embryofetal toxicity and genotoxic effects on sperm cells, advise male patients with pregnant partners or female partners of reproductive potential to use condoms during treatment with temozolomide and for 3 months after the last dose [see Use in Specific Populations (8.1), Nonclinical Toxicology (13.1)]. Advise male patients not to donate semen during treatment with temozolomide and for 3 months after the last dose.

Infertility

Temozolomide may impair male fertility [see Nonclinical Toxicology (13.1)] . Limited data from male patients show changes in sperm parameters during treatment with temozolomide; however, no information is available on the duration or reversibility of these changes.

8.4 Pediatric Use

Safety and effectiveness of temozolomide have not been established in pediatric patients. Safety and effectiveness of temozolomide capsules were assessed, but not established, in 2 open-label studies in pediatric patients aged 3 to18 years. In one study, 29 patients with recurrent brain stem glioma and 34 patients with recurrent high-grade astrocytoma were enrolled. In a second study conducted by the Children’s Oncology Group (COG), 122 patients were enrolled, including patients with medulloblastoma/PNET (29), high grade astrocytoma (23), low grade astrocytoma (22), brain stem glioma (16), ependymoma (14), other CNS tumors (9), and non-CNS tumors (9). The adverse reaction profile in pediatric patients was similar to adults.

8.5 Geriatric Use

In MK-7365-051, 15% of patients with newly diagnosed glioblastoma were 65 years and older. This study did not include sufficient numbers of patients aged 65 years and older to determine differences in effectiveness from younger patients. No overall differences in safety were observed between patients ≥65 years and younger patients.

The CATNON trial did not include sufficient numbers of patients aged 65 years and older to determine differences in safety or effectiveness when compared to younger patients.

In MK-7365-006, 4% of patients with refractory anaplastic astrocytoma were 70 years and older. This study did not include sufficient numbers of patients aged 70 years and older to determine differences in effectiveness from younger patients. Patients 70 years and older had a higher incidence of Grade 4 neutropenia (25%) and Grade 4 thrombocytopenia (20%) in the first cycle of therapy than patients less than 70 years of age [see Warnings and Precautions (5.1), Adverse Reactions (6.1)].

In the entire safety database for which hematologic data exist (N=932), 7% (4/61) and 10% (6/63) of patients >70 years experienced Grade 4 neutropenia or thrombocytopenia in the first cycle, respectively. For patients ≤70 years, 7% (62/871) and 6% (48/879) experienced Grade 4 neutropenia or thrombocytopenia in the first cycle, respectively. Pancytopenia, leukopenia, and anemia also occurred.

8.6 Renal Impairment

No dosage adjustment is recommended for patients with creatinine clearance (CLcr) of 36 to 130 mL/min/m^2 [see Clinical Pharmacology (12.3)]. The recommended dose of temozolomide capsules has not been established for patients with severe renal impairment (CLcr < 36 mL/min/m^2) or for patients with end-stage renal disease on dialysis.

8.7 Hepatic Impairment

No dosage adjustment is recommended for patients with mild to moderate hepatic impairment (Child Pugh class A and B) [see Clinical Pharmacology (12.3)]. The recommended dose of temozolomide has not been established for patients with severe hepatic impairment (Child-Pugh class C).

10 OVERDOSAGE

Dose-limiting toxicity was myelosuppression and was reported with any dose but is expected to be more severe at higher doses. An overdose of 2000 mg per day for 5 days was taken by one patient and the adverse reactions reported were pancytopenia, pyrexia, multi-organ failure, and death. There are reports of patients who have taken more than 5 days of treatment (up to 64 days), with adverse reactions reported including myelosuppression, which in some cases was severe and prolonged, and infections and resulted in death. In the event of an overdose, monitor complete blood count and provide supportive measures as necessary.

11 DESCRIPTION

Temozolomide is an alkylating drug. The chemical name of temozolomide is 3,4-dihydro-3-methyl-4-oxoimidazo[5,1d]- as-tetrazine-8-carboxamide. The structural formula of temozolomide is:

The material is a white to light tan or light pink powder with a molecular formula of C6H6N6O2and a molecular weight of 194.15. The molecule is stable at acidic pH (<5) and labile at pH >7; hence temozolomide can be administered orally. The prodrug, temozolomide, is rapidly hydrolyzed to the active 5-(3-methyltriazen-1-yl) imidazole-4-carboxamide (MTIC) at neutral and alkaline pH values, with hydrolysis taking place even faster at alkaline pH.

Temozolomide capsules, USP

Temozolomide capsules, USP for oral use contains either 5 mg, 20 mg, 100 mg, 140 mg, 180 mg, or 250 mg of temozolomide.

The inactive ingredients are as follows:

Temozolomide capsules 5 mg:lactose anhydrous (168 mg), colloidal anhydrous silica (1 mg), sodium starch glycolate (16 mg), tartaric acid (7 mg), and stearic acid (3 mg).

Temozolomide capsules 20 mg:lactose anhydrous (14.6 mg), colloidal anhydrous silica (0.2 mg), sodium starch glycolate (3.2 mg), tartaric acid (1.4 mg), and stearic acid (0.6 mg).

Temozolomide capsules 100 mg:lactose anhydrous (73 mg), colloidal anhydrous silica (1 mg), sodium starch glycolate (16 mg), tartaric acid (7 mg), and stearic acid (3 mg).

Temozolomide capsules 140 mg:lactose anhydrous (102.2 mg), colloidal anhydrous silica (1.4 mg), sodium starch glycolate (22.4 mg), tartaric acid (9.8 mg), and stearic acid (4.2 mg).

Temozolomide capsules 180 mg:lactose anhydrous (131.4 mg), colloidal anhydrous silica (1.8 mg), sodium starch glycolate (28.8 mg), tartaric acid (12.6 mg), and stearic acid (5.4 mg).

Temozolomide capsules 250 mg:lactose anhydrous (182.5 mg), colloidal anhydrous silica (2.5 mg), sodium starch glycolate (40 mg), tartaric acid (17.5 mg), and stearic acid (7.5 mg).

The body of the capsules is made of gelatin, and is white. The body of 250 mg capsule contain additionally sodium lauryl sulfate. The cap is also made of gelatin, and the colors vary based on the dosage strength. The capsule body and cap are imprinted with pharmaceutical branding ink, which contains black iron oxide, potassium hydroxide and shellac.

Temozolomide capsules 5 mg:The green cap contains gelatin, titanium dioxide, iron oxide yellow and FD&C Blue 2.

Temozolomide capsules 20 mg:The yellow cap contains gelatin, titanium dioxide and iron oxide yellow.

Temozolomide capsules 100 mg:The pink cap contains gelatin, titanium dioxide and iron oxide red.

Temozolomide capsules 140 mg:The transparent blue cap contains gelatin and FD&C Blue 2.

Temozolomide capsules 180 mg:The maroon cap contains gelatin, iron oxide red, iron oxide yellow and titanium dioxide.

Temozolomide capsules 250 mg:The white cap contains gelatin, titanium dioxide and sodium lauryl sulfate.

12 CLINICAL PHARMACOLOGY

12.1 Mechanism of Action

Temozolomide is not directly active but undergoes rapid nonenzymatic conversion at physiologic pH to the reactive compound 5-(3-methyltriazen-1-yl)-imidazole-4-carboxamide (MTIC). The cytotoxicity of MTIC is thought to be primarily due to DNA alkylation, mainly at the O^6and N^7positions of guanine, which causes DNA double strand breaks and results in programmed cell death.

12.2 Pharmacodynamics

Temozolomide exposure-response relationships and the time course of pharmacodynamic response are unknown.

12.3 Pharmacokinetics

Following a single oral dose of 150 mg/m^2, the mean Cmaxis 7.5 mcg/mL for temozolomide and 282 ng/mL for MTIC. The mean AUC is 23.4 mcg·hr/mL for temozolomide and 864 ng·hr/mL for MTIC.

Following a single 90-minute intravenous infusion of 150 mg/m^2, the mean Cmaxis 7.3 mcg/mL for temozolomide and 276 ng/mL for MTIC. The mean AUC is 24.6 mcg·hr/mL for temozolomide and 891 ng·hr/mL for MTIC.

Temozolomide exhibits linear kinetics over the therapeutic dosing range of 75 mg/m^2/day to 250 mg/m^2/day.

Absorption

The median Tmaxis 1 hour.

Effect of Food

The mean temozolomide Cmaxand AUC decreased by 32% and 9%, respectively, and median Tmaxincreased by 2-fold (from 1 to 2.25 hours) when temozolomide capsules were administered after a modified high-fat breakfast (587 calories comprised of 1 fried egg, 2 strips of bacon, 2 slices of toast, 2 pats of butter, and 8 oz whole milk).

Distribution

Temozolomide has a mean (CV%) apparent volume of distribution of 0.4 L/kg (13%). The mean percent bound of drug-related total radioactivity is 15%.

Elimination

Clearance of temozolomide is approximately 5.5 L/hr/m^2and the mean elimination half-life is 1.8 hours.

Metabolism

Temozolomide is spontaneously hydrolyzed at physiologic pH to the active species, MTIC and to temozolomide acid metabolite. MTIC is further hydrolyzed to 5-amino-imidazole-4-carboxamide (AIC), which is known to be an intermediate in purine and nucleic acid biosynthesis, and to methylhydrazine, which is believed to be the active alkylating species. Cytochrome P450 enzymes play a minor role in the metabolism of temozolomide and MTIC. Relative to the AUC of temozolomide, the exposure to MTIC and AIC is 2.4% and 23%, respectively.

Excretion

Approximately 38% of the administered temozolomide total radioactive dose is recovered over 7 days: 38% in urine and 0.8% in feces. The majority of the recovered radioactivity in urine is unchanged temozolomide (6%), AIC (12%), temozolomide acid metabolite (2.3%), and unidentified polar metabolite(s) (17%).

Specific Populations

No clinically significant differences in the pharmacokinetics of temozolomide were observed based on age (range: 19 to 78 years), gender, smoking status (smoker vs. non-smoker), creatinine clearance (CLcr) of 36 to 130 mL/min/m^2, or mild to moderate hepatic impairment (Child Pugh class A and B). The pharmacokinetics of temozolomide has not been studied in patients with CLcr < 36 mL/min/m^2, end-stage renal disease on dialysis, or severe hepatic impairment (Child Pugh class C).

Drug Interaction Studies

Clinical Studies and Model-Informed Approaches

No clinically significant differences in the pharmacokinetics of temozolomide or MTIC were observed when co-administered with ranitidine.

No clinically significant differences in the clearance of temozolomide or MTIC were predicted when co-administered with the following drugs: valproic acid, dexamethasone, prochlorperazine, phenytoin, carbamazepine, ondansetron, histamine-2-receptor antagonists, or phenobarbital.

13 NONCLINICAL TOXICOLOGY

13.1 Carcinogenesis, Mutagenesis, Impairment of Fertility

Temozolomide is carcinogenic in rats at doses less than the maximum recommended human dose. Temozolomide induced mammary carcinomas in both males and females at doses 0.13 to 0.63 times the maximum human dose (25 to 125 mg/m^2) when administered orally on 5 consecutive days every 28 days for 6 cycles. Temozolomide also induced fibrosarcomas of the heart, eye, seminal vesicles, salivary glands, abdominal cavity, uterus, and prostate, carcinomas of the seminal vesicles, schwannomas of the heart, optic nerve, and harderian gland, and adenomas of the skin, lung, pituitary, and thyroid at doses 0.5 times the maximum daily dose. Mammary tumors were also induced following 3 cycles of temozolomide at the maximum recommended daily dose.

Temozolomide is a mutagen and a clastogen. In a reverse bacterial mutagenesis assay (Ames assay), temozolomide increased revertant frequency in the absence and presence of metabolic activation. Temozolomide was clastogenic in human lymphocytes in the presence and absence of metabolic activation.

Temozolomide impairs male fertility. Temozolomide caused syncytial cells/immature sperm formation at doses of 50 and 125 mg/m^2(0.25 and 0.63 times the human dose of 200 mg/m^2) in rats and dogs, respectively, and testicular atrophy in dogs at 125 mg/m^2.

13.2 Animal Toxicology and/or Pharmacology

Toxicology studies in rats and dogs identified a low incidence of hemorrhage, degeneration, and necrosis of the retina at temozolomide doses equal to or greater than 125 mg/m^2(0.63 times the human dose of 200 mg/m^2). These changes were most commonly seen at doses where mortality was observed.

14 CLINICAL STUDIES

14.1 Newly Diagnosed Glioblastoma

The efficacy of temozolomide was evaluated in MK-7365-051 (NCT00006353), a randomized (1:1), multicenter, open-label trial. Eligible patients were required to have newly diagnosed glioblastoma. Patients were randomized to receive either radiation therapy alone or concomitant temozolomide 75 mg/m^2once daily starting the first day of radiation therapy and continuing until the last day of radiation therapy for 42 days (with a maximum of 49 days), followed by temozolomide 150 mg/m^2or 200 mg/m^2once daily on Days 1 to 5 of each 28-day cycle, starting 4 weeks after the end of radiation therapy and continuing for 6 cycles. In both arms, focal radiation therapy was delivered as 60 Gy/30 fractions and included radiation to the tumor bed or resection site with a 2-to 3-cm margin. PCP prophylaxis was required during the concomitant phase, regardless of lymphocyte count and continued until recovery of lymphocyte count to Grade 1 or less. The major efficacy outcome measure was overall survival.

A total of 573 patients were randomized, 287 to temozolomide and radiation therapy and 286 to radiation therapy alone. At the time of disease progression, temozolomide was administered as salvage therapy in 161 patients of the 282 (57%) in the radiation therapy alone arm and 62 patients of the 277 (22%) in the temozolomide and radiation therapy arm.

The addition of concomitant and maintenance temozolomide to radiation therapy for the treatment of patients with newly diagnosed glioblastoma showed a statistically significant improvement in overall survival compared to radiotherapy alone (Figure 1). The hazard ratio (HR) for overall survival was 0.63 (95% CI: 0.52, 0.75) with a log-rank P<0.0001 in favor of the temozolomide arm. The median overall survival was 14.6 months in the temozolomide arm and 12.1 months for radiation therapy alone arm.

FIGURE 1: Kaplan-Meier Curves for Overall Survival (ITT Population) in Patients with Newly Diagnosed Glioblastoma in MK-7365-051

14.2 Anaplastic Astrocytoma

Newly Diagnosed Anaplastic Astrocytoma

The efficacy of temozolomide for the adjuvant treatment of newly diagnosed anaplastic astrocytoma was derived from studies of temozolomide in the published literature. Temozolomide was evaluated in CATNON (NCT00626990), a randomized, open-label, multicenter trial, where the major efficacy outcome measure was overall survival.

Refractory Anaplastic Astrocytoma

The efficacy of temozolomide was evaluated in Study MK-7365-006, a single-arm, multicenter trial. Eligible patients had anaplastic astrocytoma at first relapse and a baseline Karnofsky performance status (KPS) of 70 or greater. Patients had previously received radiation therapy and may also have previously received a nitrosourea with or without other chemotherapy. Fifty-four patients had disease progression on prior therapy with both a nitrosourea and procarbazine and their malignancy was considered refractory to chemotherapy (refractory anaplastic astrocytoma population). Temozolomide capsules were given on Days 1 to 5 of each 28-day cycle at a starting dose of 150 mg/m^2/day. If ANC was ≥1.5 x 10^9/L and platelet count was ≥100 x 10^9/L at the nadir and on Day 1 of the next cycle, the temozolomide dose was increased to 200 mg/m^2/day. The major efficacy outcome measure was progression-free survival at 6 months and the additional efficacy outcome measures were overall survival and overall response rate.

In the refractory anaplastic astrocytoma population (n=54), the median age was 42 years (range: 19 to 76); 65% were male; and 72% had a KPS of >80. Sixty-three percent of patients had surgery other than a biopsy at the time of initial diagnosis. Of those patients undergoing resection, 73% underwent a subtotal resection and 27% underwent a gross total resection. Eighteen percent of patients had surgery at the time of first relapse. The median time from initial diagnosis to first relapse was 13.8 months (range: 4.2 months to 6.3 years).

In the refractory anaplastic astrocytoma population, the overall response rate (CR+PR) was 22% (12 of 54 patients) and the complete response rate was 9% (5 of 54 patients). The median duration of all responses was 50 weeks (range: 16 to 114 weeks) and the median duration of complete responses was 64 weeks (range: 52 to 114 weeks). In this population, progression-free survival at 6 months was 45% (95% CI: 31%, 58%) and progression-free survival at 12 months was 29% (95% CI: 16%, 42%). Median progression-free survival was 4.4 months. Overall survival at 6 months was 74% (95% CI: 62%, 86%) and 12-month overall survival was 65% (95% CI: 52%, 78%). Median overall survival was 15.9 months.

15 REFERENCES

1. “OSHA Hazardous Drugs.” OSHA. http://www.osha.gov/hazardous-drugs

16 HOW SUPPLIED/STORAGE AND HANDLING

Temozolomide is a hazardous drug. Follow applicable special handling and disposal procedures.^1

Temozolomide capsules, USP

Temozolomide capsules, USP are supplied in amber glass bottles with child-resistant polypropylene caps and child-resistant sachet packs containing the following capsule strengths:

Temozolomide Capsules 5 mg:have white bodies with green caps. The capsule body is imprinted with '5'. The cap is imprinted with 'TMZ'.
They are supplied as follows:
Amber Glass Bottles
5 count – NDC 16729-048-53
14 count – NDC 16729-048-54
Sachet Packs (Carton Contains Individual Sachet with One Capsule each):
5 count – NDC 16729-048-31
14 count – NDC 16729-048-04

Temozolomide Capsules 20 mg:have white bodies with yellow caps. The capsule body is imprinted with '20'. The cap is imprinted with 'TMZ'.
They are supplied as follows:
Amber Glass Bottles
5 count – NDC 16729-049-53
14 count – NDC 16729-049-54
Sachet Packs (Carton Contains Individual Sachet with One Capsule each):
5 count – NDC 16729-049-31
14 count – NDC 16729-049-04

Temozolomide Capsules 100 mg:have white bodies with pink caps. The capsule body is imprinted with '100'. The cap is imprinted with 'TMZ'.
They are supplied as follows:
Amber Glass Bottles
5 count – NDC 16729-050-53
14 count – NDC 16729-050-54
Sachet Packs (Carton Contains Individual Sachet with One Capsule each):
5 count – NDC 16729-050-31
14 count – NDC 16729-050-04

Temozolomide Capsules 140 mg:have white bodies with transparent blue caps. The capsule body is imprinted with '140'. The cap is imprinted with 'TMZ'.
They are supplied as follows:
Amber Glass Bottles
5 count – NDC 16729-129-53
14 count – NDC 16729-129-54
Sachet Packs (Carton Contains Individual Sachet with One Capsule each):
5 count – NDC 16729-129-31
14 count – NDC 16729-129-04

Temozolomide Capsules 180 mg:have white bodies with maroon caps. The capsule body is imprinted with '180'. The cap is imprinted with 'TMZ'.
They are supplied as follows:
Amber Glass Bottles
5 count – NDC 16729-130-53
14 count – NDC 16729-130-54
Sachet Packs (Carton Contains Individual Sachet with One Capsule each):
5 count – NDC 16729-130-31
14 count – NDC 16729-130-04

Temozolomide Capsules 250 mg:have white bodies with white caps. The capsule body is imprinted with '250'. The cap is imprinted with 'TMZ'.
They are supplied as follows:
Amber Glass Bottles
5 count – NDC 16729-051-53
Sachet Packs (Carton Contains Individual Sachet with One Capsule each):
5 count – NDC 16729-051-31

Store temozolomide capsules at 20° to 25°C (68° to 77°F); excursions permitted to 15°C to 30°C (59°F to 86°F).

17 PATIENT COUNSELING INFORMATION

Advise the patient to read the FDA-approved patient labeling (Patient Information).

Myelosuppression
Inform patients that temozolomide can cause low blood cell counts and the need for frequent monitoring of blood cell counts. Advise patients to contact their healthcare provider immediately for bleeding, fever, or other signs of infection [see Warnings and Precautions (5.1)] .

Hepatotoxicity
Advise patients of the increased risk of hepatotoxicity and to contact their healthcare provider immediately for signs or symptoms of hepatotoxicity. Inform patients that they will have periodic liver enzyme tests during treatment and following the last dose of temozolomide [see Warnings and Precautions (5.2)] .

Pneumocystis Pneumonia
Advise patients of the increased risk of Pneumocystis pneumonia and to contact their healthcare provider immediately for new or worsening pulmonary symptoms. Inform patients that prophylaxis for Pneumocystis pneumonia may be needed [see Dosage and Administration (2.1), Warnings and Precautions (5.3)] .

Secondary Malignancies
Advise patients of the increased risk of myelodysplastic syndrome and secondary malignancies [see Warnings and Precautions (5.4)] .

Exposure to Opened Capsules
Advise patient to not open, chew, or dissolve the capsules. If capsules are accidentally opened or damaged, advise patients to take rigorous precautions with capsule contents to avoid inhalation or contact with the skin or mucous membranes [see Warnings and Precautions (5.6)]. In case of powder contact, wash the affected area with water immediately [see Dosage and Administration (2.4)] .

Embryo-Fetal Toxicity
Advise pregnant women and females of reproductive potential of the potential risk to a fetus. Advise females to inform their healthcare provider of a known or suspected pregnancy [see Warnings and Precautions (5.5), Use in Specific Populations (8.1)] .

Advise females of reproductive potential to use effective contraception during treatment with temozolomide and for 6 months after the last dose [see Use in Specific Populations (8.3)] .

Advise male patients with pregnant partners or female partners of reproductive potential to use condoms during treatment with temozolomide and for 3 months after the last dose [see Use in Specific Populations (8.3), Nonclinical Toxicology (13.1)] .

Advise male patients not to donate semen during treatment with temozolomide and for 3 months after the last dose [see Use in Specific Populations (8.3), Nonclinical Toxicology (13.1)] .

Lactation
Advise women not to breastfeed during treatment with temozolomide and for 1 week after the last dose [see Use in Specific Populations (8.2)] .

Infertility
Advise males of reproductive potential that temozolomide may impair fertility [see Use in Specific Populations (8.3), Nonclinical Toxicology (13.1)] .

Manufactured For:
Accord Healthcare, Inc.,
8041 Arco Corporate Drive,
Suite 200,
Raleigh, NC 27617,
USA.

Manufactured By:
Intas Pharmaceuticals Limited,
Ahmedabad -380 054, India.
10 1475 6 6030879
Issued June 2024

Patient Information

Temozolomide Capsules
(TEM-oh-ZOE-loe-mide)

What is temozolomide capsule?

Temozolomide capsule is a prescription medicine used to treat adults with certain brain cancer tumors.

It is not known if temozolomide capsule is safe and effective in children.

Do not take temozolomide capsules if you:

- have had an allergic reaction to temozolomide or any of the other ingredients in temozolomide capsules. See the end of this leaflet for a list of ingredients in temozolomide capsules. Symptoms of an allergic reaction with temozolomide capsules may include: a red itchy rash, or a severe allergic reaction, such as trouble breathing, swelling of the face, throat, or tongue, or severe skin reaction. If you are not sure, ask your healthcare provider.
- have had an allergic reaction to dacarbazine (DTIC), another cancer medicine.

Before taking or receiving temozolomide capsules, tell your healthcare provider about all of your medical conditions, including if you:

- have kidney problems
- have liver problems
- are pregnant or plan to become pregnant. Temozolomide capsules can harm your unborn baby and cause birth defects. Females who can become pregnant:
  - You should not become pregnant during treatment with temozolomide capsules.
  - You should use an effective form of birth control (contraception) during treatment and for 6 months after your last dose of temozolomide capsules.
  - Your healthcare provider should do a pregnancy test to make sure that you are not pregnant before you start taking temozolomide capsules.
  - Tell your healthcare provider right away if you become pregnant or think you may be pregnant during treatment with temozolomide capsules.
    Males with a female partner who is pregnant or who can become pregnant:
  - Use a condom for birth control (contraception) during treatment and for 3 months after taking your last dose of temozolomide capsules.
  - Do notdonate semen during treatment and for 3 months after your last dose of temozolomide capsules.
- are breastfeeding or plan to breastfeed. It is not known if temozolomide passes into your breast milk. Do not breastfeed during treatment and for 1 week after your last dose of temozolomide capsules.

Tell your doctor about all the medicines you take,including prescription and non-prescription medicines, vitamins, and herbal supplements.

Know the medicines you take. Keep a list of them and show it to your healthcare provider and pharmacist when you get a new medicine.

How should I take temozolomide capsules?

Temozolomide capsules may be taken by mouth as a capsule.

Your healthcare provider will decide the best way for you to take temozolomide capsules.

- If your healthcare provider prescribes temozolomide capsules for you, take the capsules exactly as prescribed.

There are 2 common dosing schedules for taking or receiving temozolomide capsules depending on the type of brain cancer tumor that you have.

- People with certain brain cancer tumors take or receive temozolomide capsules:
  - 1 time each day for 42 to 49 days in a row, along with receiving radiation treatment. This is 1 cycle of treatment.
    After this, your healthcare provider may prescribe 6 more cycles of temozolomide capsules as “maintenance” treatment. For each of these cycles, you take or receive temozolomide capsules 1 time each day for 5 days in a row and then you stop taking it for the next 23 days. This is a 28-day maintenance treatment cycle.
- People with certain other brain cancer tumors take or receive temozolomide capsules:
  - 1 time each day for 5 days in a row only, and then stop taking it for the next 23 days. This is 1 cycle of treatment (28 days).
  - Your healthcare provider will watch your progress on temozolomide capsules and decide how long you should take it.
- If your healthcare provider prescribes a treatment regimen that is different from the information in this leaflet, make sure you follow the instructions given to you by your healthcare provider.
- Your healthcare provider may change your dose of temozolomide capsules, or tell you to stop temozolomide capsules for a short period of time or permanently if you have certain side effects.
- Your healthcare provider will decide how many treatment cycles of temozolomide capsules that you will receive, depending on how you respond to and tolerate treatment.

Temozolomide capsules:

- Take temozolomide capsules exactly as your healthcare provider tells you to.
- Temozolomide capsules come in different strengths. Each strength has a different color cap. Your healthcare provider may prescribe more than 1 strength of temozolomide capsules for you, so it is important that you understand how to take your medicine the right way. Be sure that you understand exactly how many capsules you need to take on each day of your treatment, and what strengths to take. This may be different whenever you start a new cycle.
- Do not take more temozolomide capsules than prescribed.
- Talk to your healthcare provider or pharmacist before taking your dose if you are not sure how much temozolomide capsules to take. This will help to prevent taking too much temozolomide capsules and decrease your chances of getting serious side effects.
- Take each day’s dose of temozolomide capsules at one time, with a full glass of water.
- Take temozolomide capsules at the same time each day.
- Take temozolomide capsules the same way each time, either with food or without food.
- Swallow temozolomide capsules whole with water. Do notopen, chew, or dissolve the contents of the capsules.
- If temozolomide capsules are accidentally opened or damaged, be careful not to breathe in (inhale) the powder from the capsules or get the powder on your skin or mucous membranes (for example, in your nose or mouth). If contact with any of these areas happens, wash the area with water right away.
- To help reduce nausea and vomiting, try to take temozolomide capsules on an empty stomach or at bedtime. Your healthcare provider may prescribe medicine to help prevent or treat nausea, or other medicines to reduce side effects with temozolomide capsules.
- See your healthcare provider regularly to check your progress. Your healthcare provider will check you for side effects.
- If you take more temozolomide capsules than prescribed, call your healthcare provider or get emergency medical help right away.

What are the possible side effects of temozolomide capsules?

Temozolomide capsules can cause serious side effects, including:

- Decreased blood cell counts.Temozolomide capsules can affect your bone marrow and cause you to have decreased blood cell counts. Decreased white blood cell count, red blood cell count and platelet count are common with temozolomide capsules but it can also be severe and lead to death. Some people need to be hospitalized or need to receive transfusions to treat their decreased blood cell counts.
  - Your healthcare provider will do blood tests regularly to check your blood cell counts before you start and during treatment with temozolomide capsules.
  - Your healthcare provider may need to change the dose of temozolomide capsules, or when you get it depending on your blood cell counts.
  - People who are age 70 or older and women have a higher risk for developing decreased blood cell counts during treatment with temozolomide capsules.
- Liver problems. Liver problems can happen with temozolomide capsules and can sometimes be severe and lead to death.Your healthcare provider will do blood tests to check your liver function before you start taking temozolomide capsules, during treatment, and about 2 to 4 weeks after your last dose of temozolomide capsules.
- Pneumocystis pneumonia (PCP).PCP is an infection that people can get when their immune system is weak. Temozolomide capsules decreases white blood cells, which makes your immune system weaker and can increase your risk of getting PCP.
  - People who are taking steroid medicines or who stay on temozolomide capsules for a longer period of time may have an increased risk of getting PCP infection.
  - Anyone who takes temozolomide capsules will be watched carefully by their healthcare provider for low blood cell counts and this infection.
  - Tell your healthcare provider if you have any of the following signs and symptoms of PCP infection: shortness of breath, or fever, chills, dry cough.
- Secondary Cancers.Blood problems such as myelodysplastic syndrome (MDS) and new cancers (secondary cancers), including a certain kind of leukemia, can happen in people who take temozolomide capsules. Your healthcare provider will monitor you for this.

Common side effects of temozolomide capsules include:

- hair loss
- feeling tired
- nausea and vomiting.

- headache
- constipation
- loss of appetite
- convulsions

Temozolomide capsules can affect fertility in males and may affect your ability to father a child. Talk with your healthcare provider if fertility is a concern for you.
Tell your healthcare provider about any side effect that bothers you or that does not go away.

These are not all the possible side effects of temozolomide capsules. For more information, ask your healthcare provider or pharmacist.

Call your doctor for medical advice about side effects. You may report side effects to FDA at 1-800-FDA-1088.

How should I store temozolomide capsules?

- Store temozolomide capsules at 77°F (controlled room temperature). Storage at 68°F to 77°F (20°C to 25°C) is permitted occasionally.
- Temozolomide capsules comes in a child-resistant package.

Keep temozolomide capsules and all medicines out of the reach of children.

General information about the safe and effective use of temozolomide capsules.

Medicines are sometimes prescribed for purposes other than those listed in a Patient Information leaflet. Do not use temozolomide capsules for a condition for which it was not prescribed. Do not give temozolomide capsules to other people, even if they have the same symptoms that you have. It may harm them. You can ask your pharmacist or healthcare provider for information about temozolomide capsules that is written for health professionals.

What are the ingredients in temozolomide capsules?
Temozolomide capsules:

Active ingredient:temozolomide.

Inactive ingredients:lactose anhydrous, colloidal anhydrous silica, sodium starch glycolate, tartaric acid, stearic acid.

The body of the capsules is made of gelatin and is white. The body of 250 mg capsule contain additionally sodium lauryl sulfate. The cap is also made of gelatin, and the colors vary based on the dosage strength. The capsule body and cap are imprinted with pharmaceutical branding ink, which contains black iron oxide, potassium hydroxide and shellac.

Temozolomide capsules 5 mg: The green cap contains gelatin, titanium dioxide, iron oxide yellow and FD&C Blue 2.

Temozolomide capsules 20 mg: The yellow cap contains gelatin, iron oxide yellow and titanium dioxide.

Temozolomide capsules 100 mg: The pink cap contains gelatin, titanium dioxide and iron oxide red.

Temozolomide capsules 140 mg: The transparent blue cap contains gelatin and FD&C Blue 2.

Temozolomide capsules 180 mg: The maroon cap contains gelatin, iron oxide red, iron oxide yellow and titanium dioxide.

Temozolomide capsules 250 mg: The white cap contains gelatin, titanium dioxide and sodium lauryl sulfate.

®The brands listed are trademarks of their respective owners.

Manufactured For:
Accord Healthcare, Inc.,
8041 Arco Corporate Drive,
Suite 200,
Raleigh, NC 27617,
USA.

Manufactured By:
Intas Pharmaceuticals Limited,
Ahmedabad -380 054, India.
For more information, go to www.accordhealthcare.us or call Accord Healthcare at 1-866-941-7875.
10 1475 6 6030879

This Patient Information has been approved by the U.S. Food and Drug Administration.

Revised: 6/2024

Temozolomide Capsules

PHARMACIST:Dispense enclosed Patient Package Insert to each patient.

PHARMACIST INFORMATION SHEET

IMPORTANT DISPENSING INFORMATION

For every patient, dispense temozolomide capsules in a separate vial or in its original package making sure each container lists the strength per capsule and that patients take the appropriate number of capsules from each package or vial.

What is temozolomide capsule?[see Full Prescribing Information, Indications and Usage (1)] .

Temozolomide is an oral alkylating agent for the treatment of newly diagnosed glioblastoma multiforme and refractory anaplastic astrocytoma.

How is temozolomide capsule dosed?[see Full Prescribing Information, Recommended Dosage and Dosage Modifications for Newly Diagnosed Glioblastoma (2.1), Recommended Dosage and Dosage Modifications for Refractory Anaplastic Astrocytoma (2.2)] .

The physician calculates the daily dose of temozolomide capsules for a given patient based on the patient’s body surface area (BSA). Round off the resulting dose to the nearest 5 mg. An example of the dosing may be as follows: the initial daily dose of temozolomide capsules in milligrams is the BSA multiplied by mg/m^2/day,(e.g., a patient with a BSA of 1.84 is 1.84 x 75 mg = 138, or 140 mg/day). Adjust the dose for subsequent cycles according to nadir neutrophil and platelet counts in the previous cycle and at the time of initiating the next cycle.

How might the dose of temozolomide capsules be modified for Refractory Anaplastic Astrocytoma?[see Full Prescribing Information, Recommended Dosage and Dosage Modifications for Refractory Anaplastic Astrocytoma (2.2)] .

The initial dose is 150 mg/m^2orally once daily for 5 consecutive days per 28-day treatment cycle. Increase the temozolomide capsules dose to 200 mg/m^2/day for 5 consecutive days per 28-day treatment cycle if both the nadir and day of dosing (Day 29, Day 1 of next cycle) absolute neutrophil counts (ANC) are greater than or equal to 1.5 x 10^9/L (1500/μL) and both the nadir and Day 29, Day 1 of next cycle platelet counts are greater than or equal to 100 x 10^9/L (100,000/μL). During treatment, obtain a complete blood count on Day 22 (21 days after the first dose) and weekly until the ANC is above 1.5 x 10^9/L (1500/μL) and the platelet count exceeds 100 x 10^9/L (100,000/μL). Do not start the next cycle of temozolomide until the ANC and platelet count exceed these levels. If the ANC falls to less than 1.0 x 10^9/L (1000/μL) or the platelet count is less than 50 x 10^9/L (50,000/μL) during any cycle, reduce the dose for the next cycle by 50 mg/m^2. Permanently discontinue temozolomide capsules in patients who are unable to tolerate a dose of 100 mg/m^2per day.

Patients should continue taking temozolomide capsules until their physician determines that their disease has progressed or until unacceptable side effects or toxicities occur. In the clinical trial, treatment could be continued for a maximum of 2 years, but the optimum duration of therapy is not known. Physicians may alter the treatment regimen for a given patient.

Dosing for Patients with Newly Diagnosed Glioblastoma Multiforme [see Full Prescribing Information, Recommended Dosage and Dosage Modifications for Newly Diagnosed Glioblastoma (2.1)] .

Concomitant Phase Treatment Schedule

Administer temozolomide capsules orally at 75 mg/m^2daily for 42 days concomitant with focal radiotherapy (60 Gy administered in 30 fractions), followed by maintenance temozolomide capsules for 6 cycles. No dose reductions are recommended; however, dose interruptions may occur based on patient tolerance. Continue the temozolomide capsules dose throughout the 42 day concomitant period up to 49 days if all of the following conditions are met: absolute neutrophil count greater than or equal to 1.5 x 10^9/L, platelet count greater than or equal to 100 x10^9/L, and nonhematological adverse reactions less than or equal to Grade 1 (except for alopecia, nausea and vomiting).During treatment,obtain a complete blood count weekly. Interrupt or discontinue temozolomide dosing during the concomitant phase according to the hematological and nonhematological toxicity criteria [see Table 1 in the Full Prescribing Information, Recommended Dosage and Dosage Modifications for Newly Diagnosed Glioblastoma (2.1)].Pneumocystis pneumonia (PCP) prophylaxis is required during the concomitant administration of temozolomide capsules and radiotherapy, and should be continued in patients who develop lymphocytopenia until resolution to Grade 1 or less.

Maintenance Phase Treatment Schedule

Four weeks after completing the temozolomide capsules and radiotherapy phase, administer temozolomide capsules for an additional 6 cycles of maintenance treatment. Dosage in Cycle 1 (maintenance) is 150 mg/m^2once daily for 5 days followed by 23 days without treatment. At the start of Cycle 2, escalate the dose to 200 mg/m^2, if the nonhematologic adverse reactions for Cycle 1 are Grade less than or equal to 2 (except for alopecia, nausea and vomiting), absolute neutrophil count (ANC) is greater than or equal to 1.5 x 10^9/L, and the platelet count is greater than or equal to 100 x 10^9/L. If the dose was not escalated at Cycle 2, do not escalate the dose in subsequent cycles. Maintain the dose at 200 mg/m^2per day for the first 5 days of each subsequent cycle except if toxicity occurs.

During treatment, obtain a complete blood count on Day 22 (21 days after the first dose) and weekly until the ANC is above 1.5 x 10^9/L (1500/μL) and the platelet count exceeds 100 x 10^9/L (100,000/μL). Do not start the next cycle of temozolomide capsules until the ANC and platelet count exceed these levels. Base dose reductions during the next cycle on the lowest blood counts and worst nonhematologic adverse reactions during the previous cycle. Apply dose reductions or discontinuations during the maintenance phase [see Table 2 in the Full Prescribing Information, Recommended Dosage and Dosage Modifications for Newly Diagnosed Glioblastoma (2.1)] .

How is temozolomide capsule taken?[See Full Prescribing Information, Preparation and Administration, temozolomide capsules (2.3).]

Advise patients to take each day’s dose with a full glass of water, preferably on an empty stomach or at bedtime. Taking the medication on an empty stomach or at bedtime may help ease nausea. If patients are also taking anti-nausea or other medications to relieve the side effects associated with temozolomide capsules, advise them to take these medications prior to and/or following administration of temozolomide capsules. Advise patients that temozolomide capsules should be swallowed whole and NEVER CHEWED. Advise patients that they SHOULD NOT open or split the capsules. If capsules are accidentally opened or damaged, advise patients to take rigorous precautions with the capsule contents to avoid inhalation or contact with the skin or mucous membranes. In case of powder contact, advise the patients to wash their hands. Advise patients to keep this medication away from children

What should the patient avoid during treatment with temozolomide capsules?[see Full Prescribing Information, Use in Specific Populations, Pregnancy (8.1), Lactation (8.2), Females and Males of Reproductive Potential (8.3)]

There are no dietary restrictions for patients taking temozolomide capsules. Temozolomide capsules may affect testicular function and may cause birth defects. Advise male patients to exercise adequate birth control measures. Advise female patients to avoid becoming pregnant while receiving this drug. Advise pregnant women of the potential risk to the fetus. Advise females of reproductive potential to use effective contraception during treatment and for at least 6 months after the last dose. Advise males of reproductive potential to use condoms during treatment and for at least 3 months after the last dose. Advise male patients not to donate semen during treatment with temozolomide capsules and for at least 3 months after the final dose. It is not known whether temozolomide is excreted into breast milk. Because of the potential for serious adverse reactions in breastfed children, advise women not to breastfeed while taking temozolomide capsules and for at least 1 week after the last dose.

What are the side effects of temozolomide capsules?[see Full Prescribing Information, Adverse Reactions (6). ]

Alopecia, fatigue, nausea, and vomiting are the most common side effects associated with temozolomide capsules. Noncumulative myelosuppression is the dose-limiting toxicity. Patients should be evaluated periodically by their physician to monitor blood counts.

Other commonly reported side effects reported by patients taking temozolomide capsulesare headache, constipation, anorexia, and convulsions.

How are temozolomide capsules supplied?[see Full Prescribing Information, How Supplied/Storage and Handling (16). ]

Temozolomide capsules are available in 5-mg, 20-mg, 100-mg, 140-mg, 180-mg, and 250-mg strengths. The capsules contain a white capsule body with a color cap, and the colors vary based on the dosage strength.

Temozolomide Capsule Strength | Color
5 mg | Green Cap
20 mg | Yellow Cap
100 mg | Pink Cap
140 mg | Transparent Blue Cap
180 mg | Maroon Cap
250 mg | White Cap

The 5-mg, 20-mg, 100-mg, 140-mg, and 180-mg capsule strengths are available in 5 count and 14 count packages. The 250-mg capsule strength is available in 5 count package.

How is temozolomide capsule dispensed?

Dispense each strength of temozolomide capsules in a separate vial or in its original package (one strength per one container). Follow the instructions below:

Based on the dose prescribed, determine the number of each strength of temozolomide capsules needed for the full 42-or 5-day cycle as prescribed by the physician. For example, in a 5-day cycle, 275 mg/day would be dispensed as five 250-mg capsules, five 20-mg capsules and five 5-mg capsules. Label each container with the appropriate number of capsules to be taken each day. Dispense to the patient, making sure each container lists the strength (mg) per capsule and that he or she understands to take the appropriate number of capsules of temozolomide capsules from each package or vial to equal the total daily dose prescribed by the physician.

How can temozolomide capsules be ordered?

Temozolomide capsules can be ordered from your wholesaler. It is important to understand if temozolomide capsules are being used as part of a 42-day regimen or as part of a 5-day course. Remember to order enough temozolomide capsules for the appropriate cycle. For example:

- a 5-day course of 360 mg/day would require the following to be ordered: two 5-count packages of 180-mg capsules.
- a 42-day course of 140 mg/day would require the following to be ordered: three 14-count packages of 140-mg capsules.

Temozolomide Capsules | NDC Number
Amber Glass Bottles:
5-mg capsules (5 count) | 16729-048-53
5-mg capsules (14 count) | 16729-048-54
20-mg capsules (5 count) | 16729-049-53
20-mg capsules (14 count) | 16729-049-54
100-mg capsules (5 count) | 16729-050-53
100-mg capsules (14 count) | 16729-050-54
140-mg capsules (5 count) | 16729-129-53
140-mg capsules (14 count) | 16729-129-54
180-mg capsules (5 count) | 16729-130-53
180-mg capsules (14 count) | 16729-130-54
250-mg capsules (5 count) | 16729-051-53
Sachet Packs (Carton Contains Individual Sachet with One Capsule each):
5-mg capsules (5 count) | 16729-048-31
5-mg capsules (14 count) | 16729-048-04
20-mg capsules (5 count) | 16729-049-31
20-mg capsules (14 count) | 16729-049-04
100-mg capsules (5 count) | 16729-050-31
100-mg capsules (14 count) | 16729-050-04
140-mg capsules (5 count) | 16729-129-31
140-mg capsules (14 count) | 16729-129-04
180-mg capsules (5 count) | 16729-130-31
180-mg capsules (14 count) | 16729-130-04
250-mg capsules (5 count) | 16729-051-31

References:
“OSHA Hazardous Drugs.” OSHA. http://www.osha.gov/SLTC/hazardousdrugs/index.

Manufactured For:
Accord Healthcare, Inc.,
8041 Arco Corporate Drive,
Suite 200,
Raleigh, NC 27617,
USA.
Manufactured By:
Intas Pharmaceuticals Limited,
Ahmedabad -380 054, India.
10 1475 6 6030879
Issued June 2024

PACKAGE LABEL

PRINCIPAL DISPLAY PANEL

Principal Display Panel- 5 mg Capsules

Amber Glass Bottle Carton

Principal Display Panel- 20 mg Capsules

Amber Glass Bottle Carton

Principal Display Panel- 100 mg Capsules

Amber Glass Bottle Carton

Principal Display Panel- 140 mg Capsules

Amber Glass Bottle Carton

Principal Display Panel- 180 mg Capsules

Amber Glass Bottle Carton

Principal Display Panel- 250 mg Capsules

Amber Glass Bottle Carton

Principal Display Panel- 5 mg Capsules

Sachet Pack Carton

Principal Display Panel- 20 mg Capsules

Sachet Pack Carton

Principal Display Panel- 100 mg Capsules

Sachet Pack Carton

Principal Display Panel- 140 mg Capsules

Sachet Pack Carton

Principal Display Panel- 180 mg Capsules

Sachet Pack Carton

Principal Display Panel- 250 mg Capsules

Sachet Pack Carton